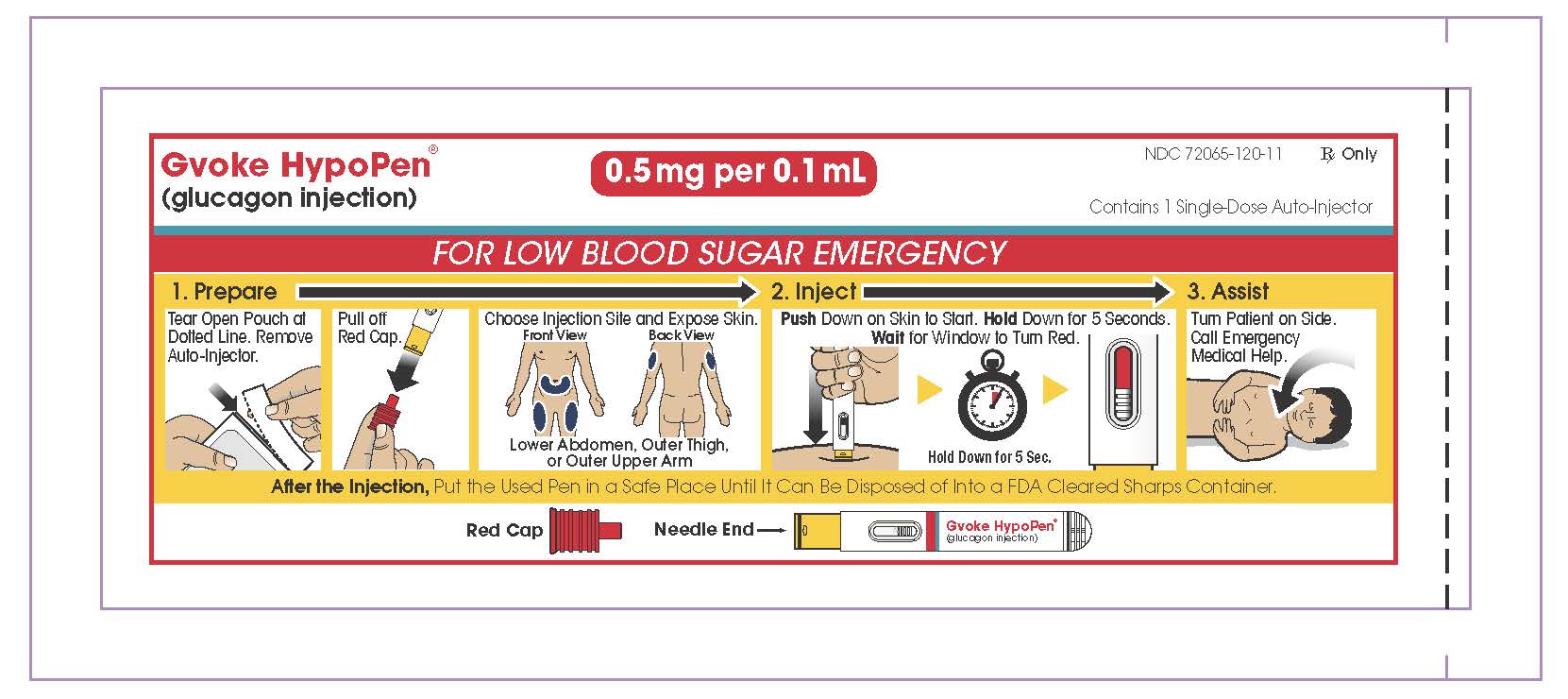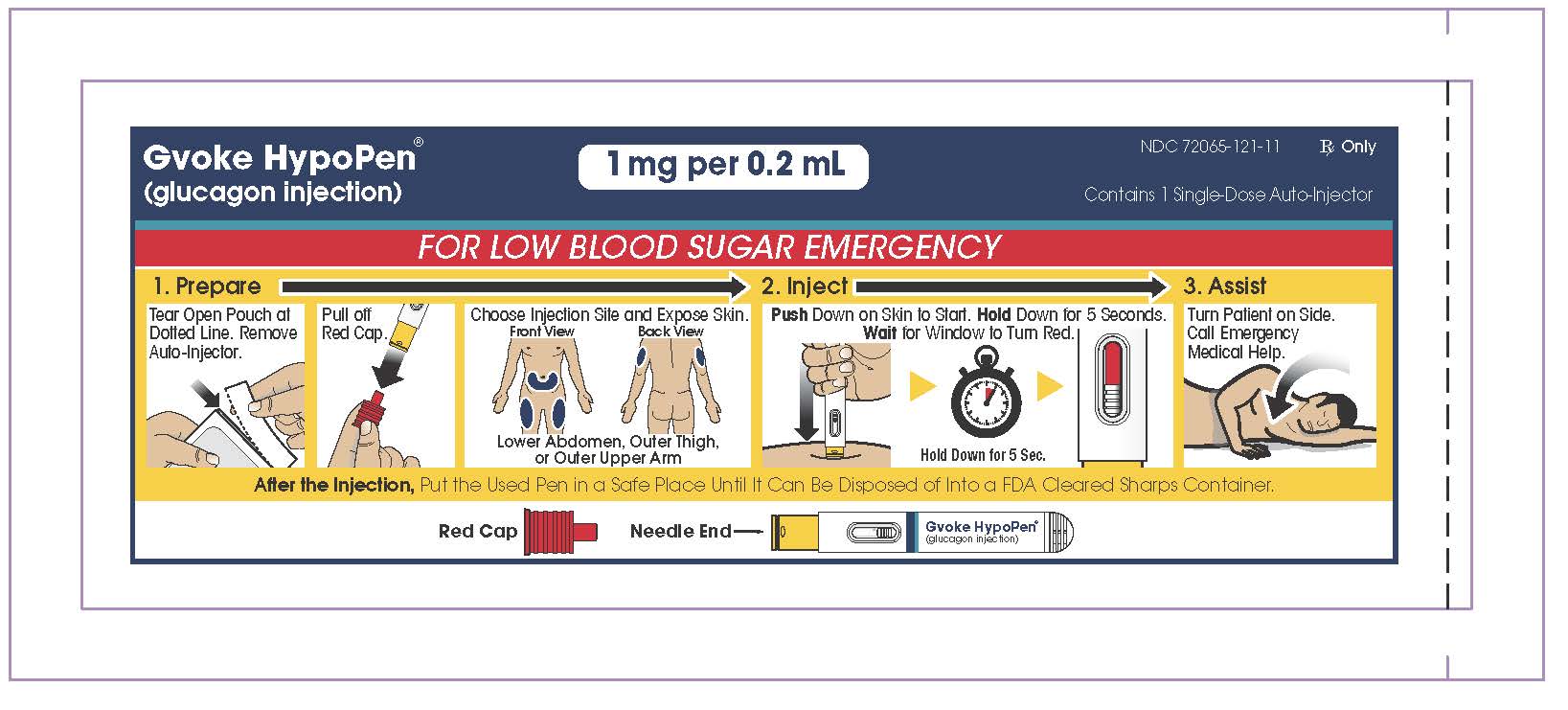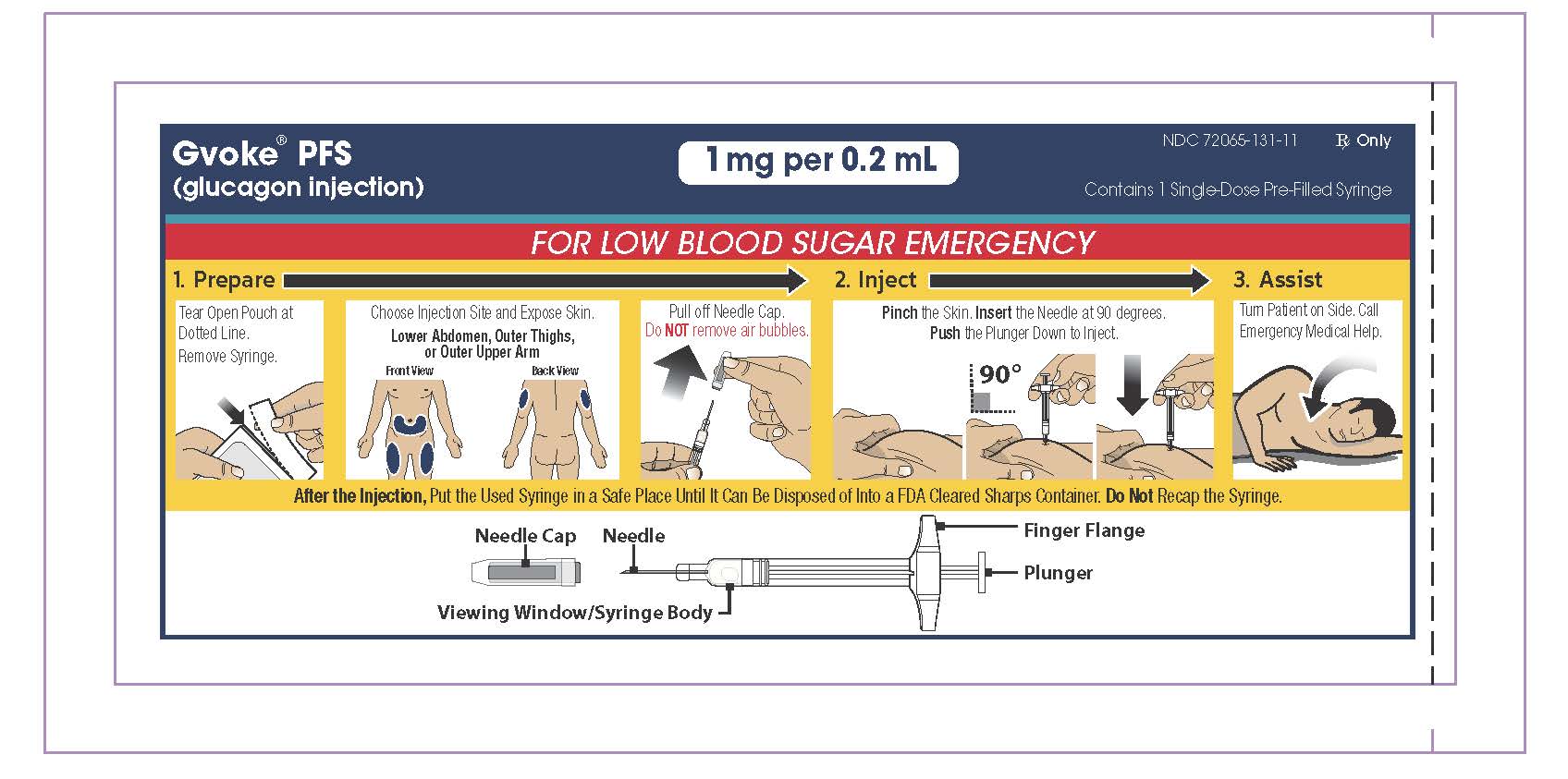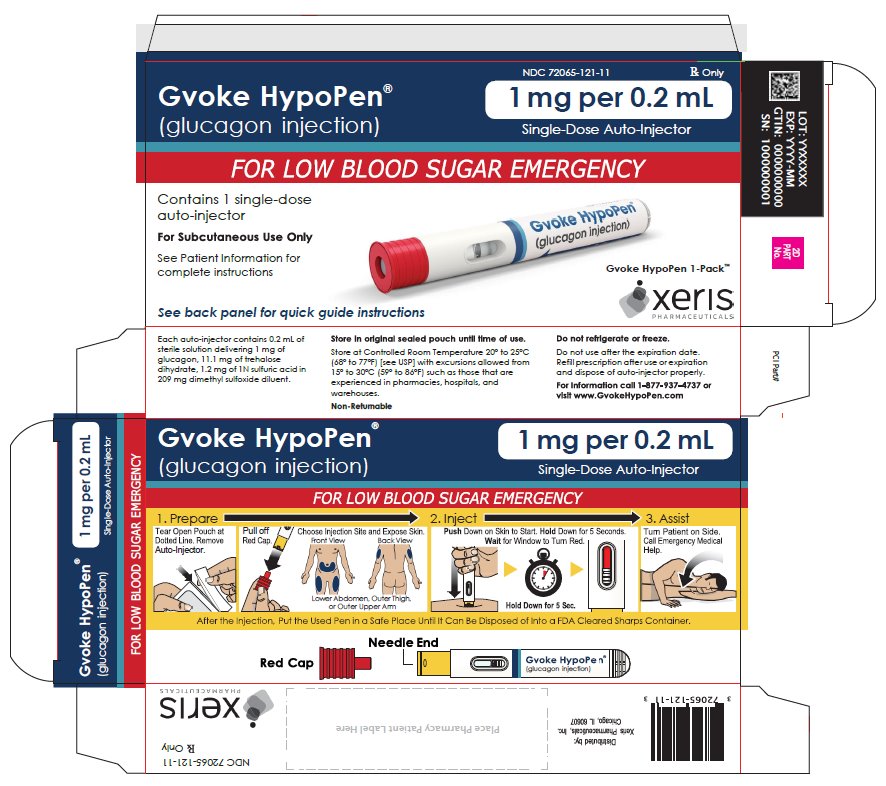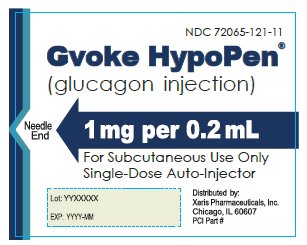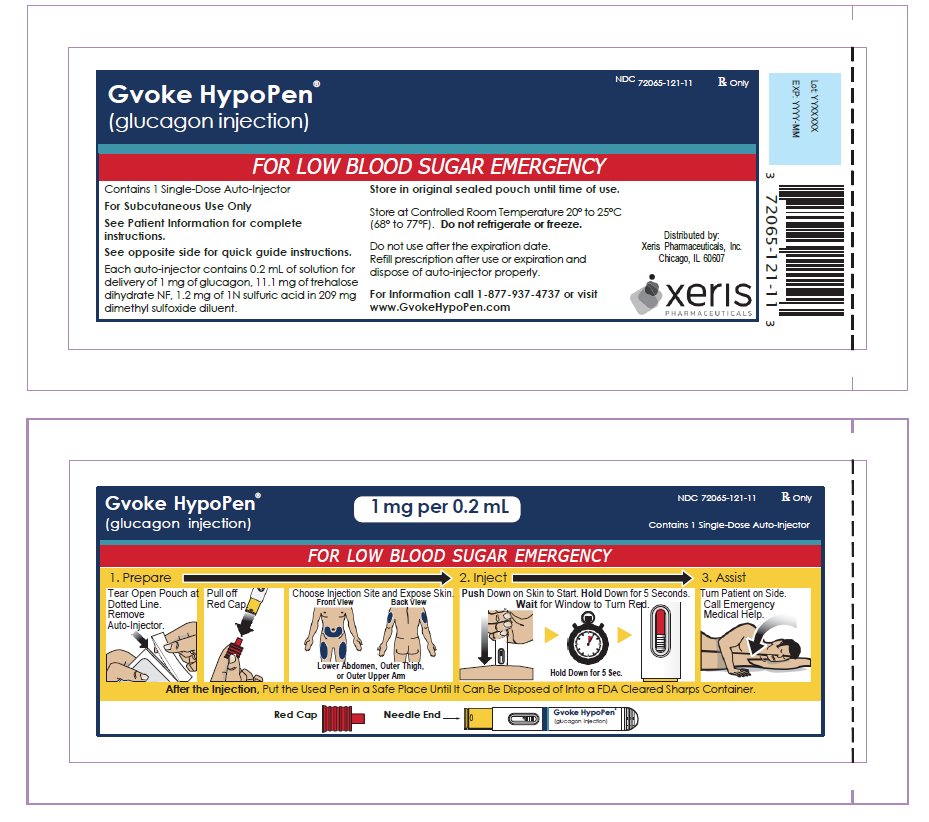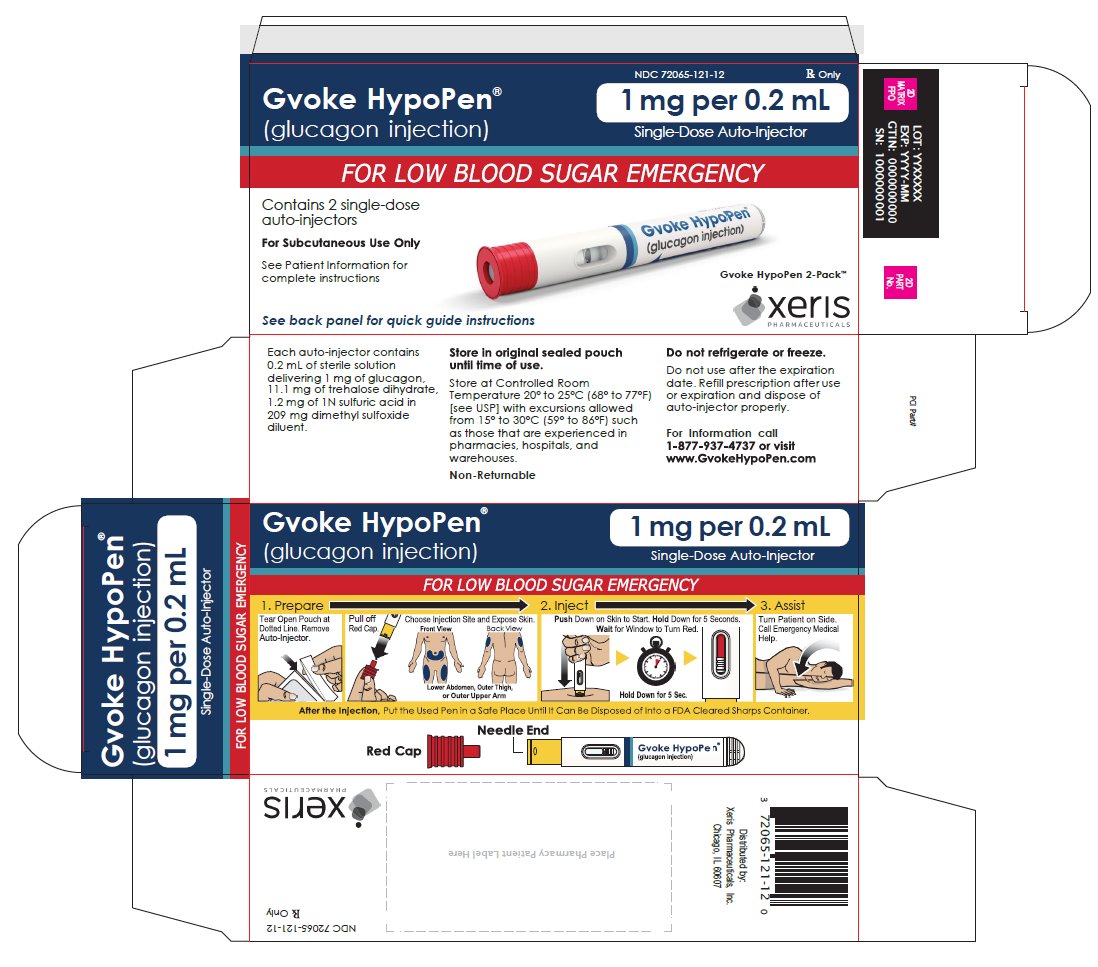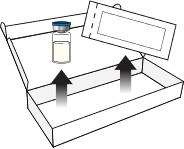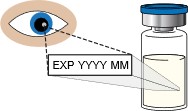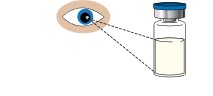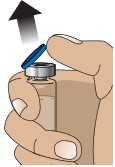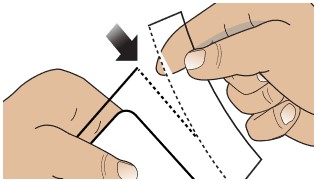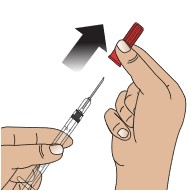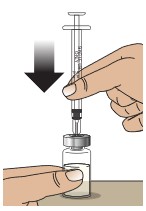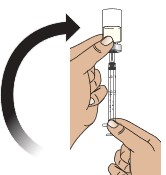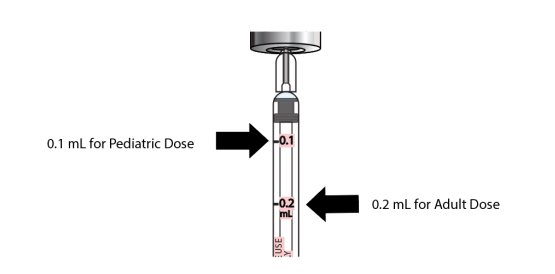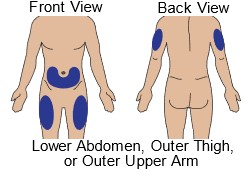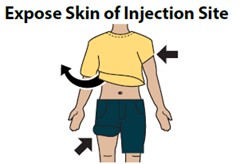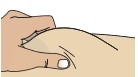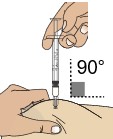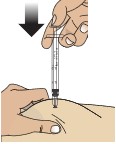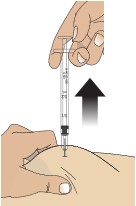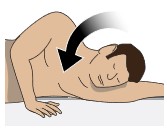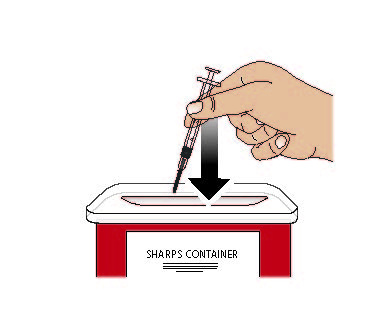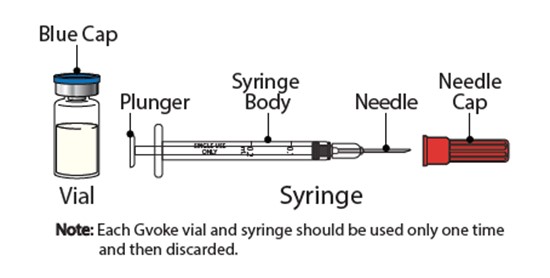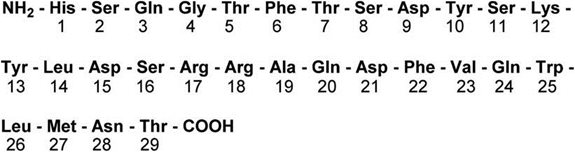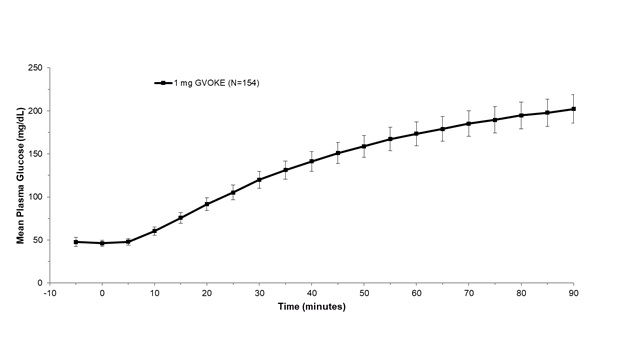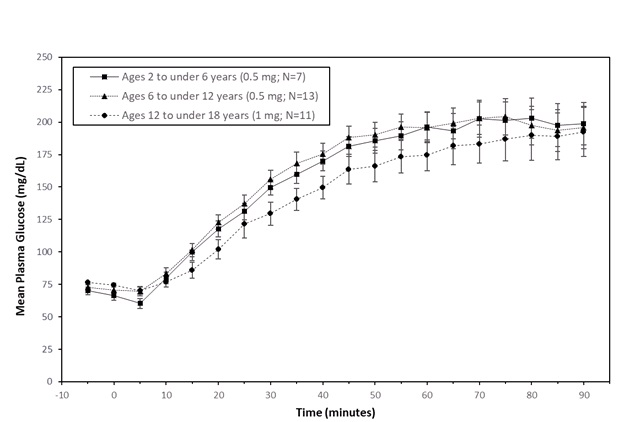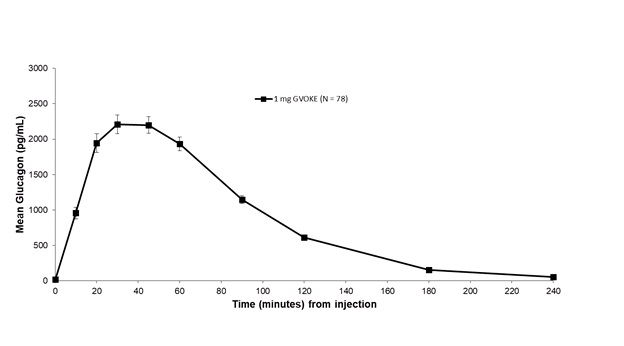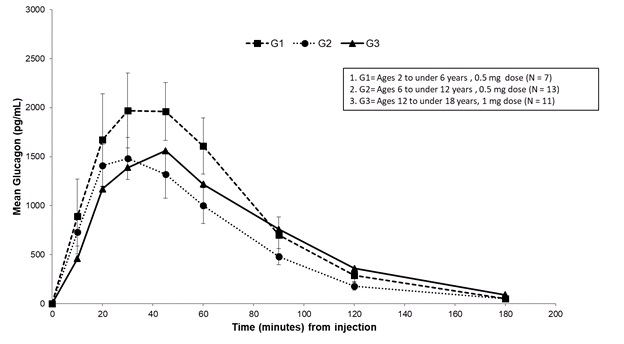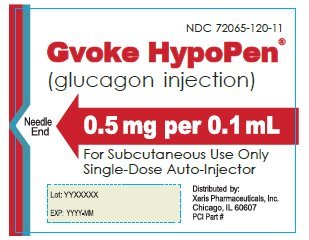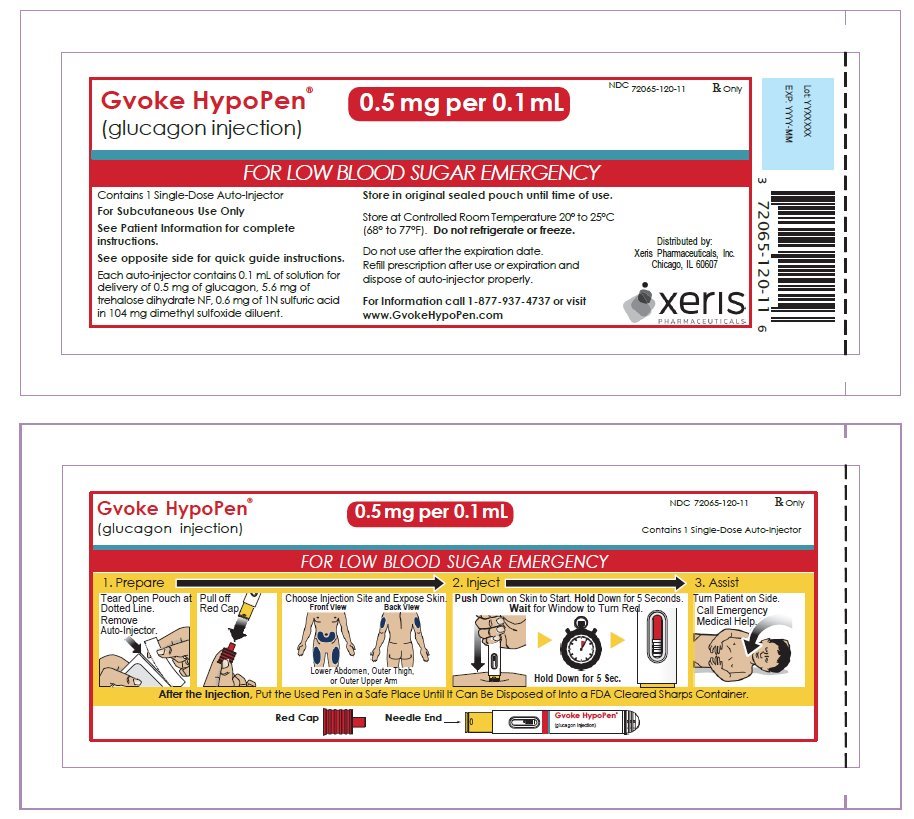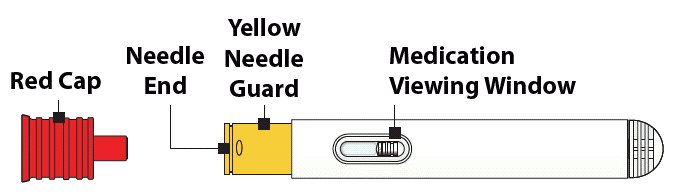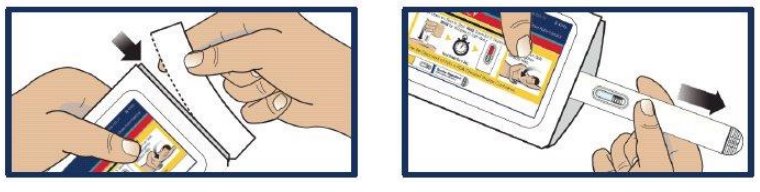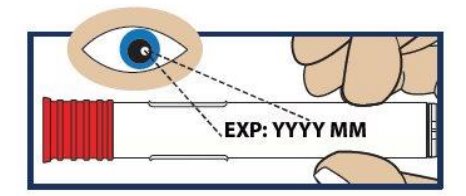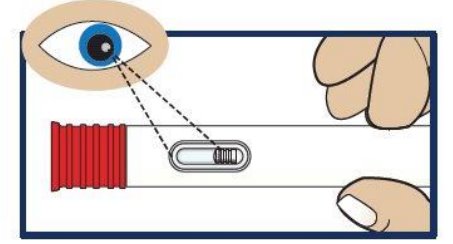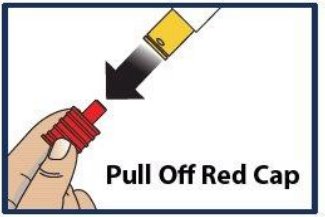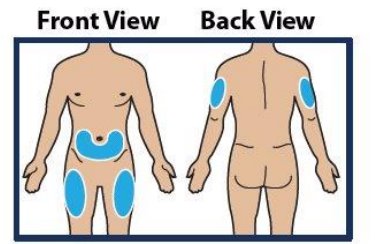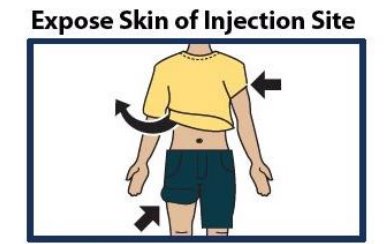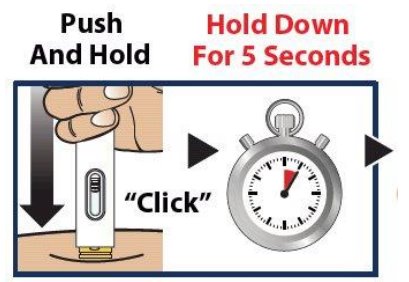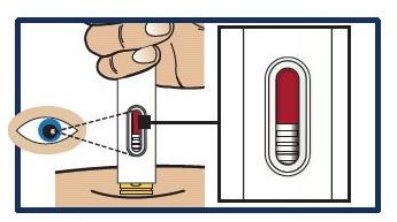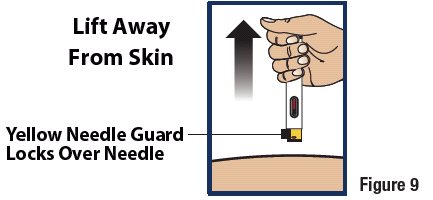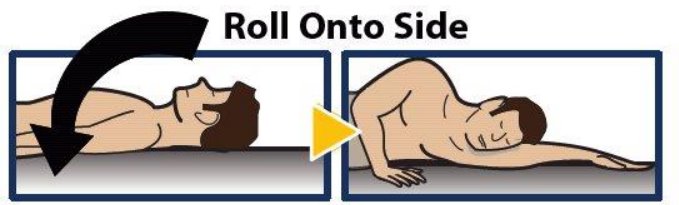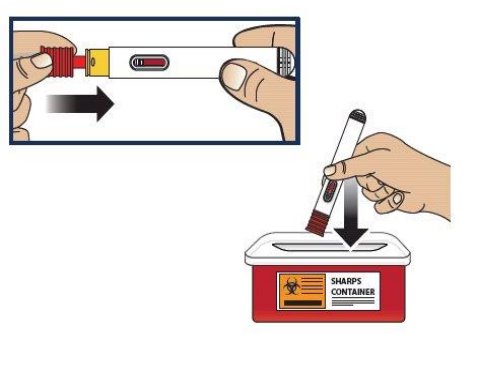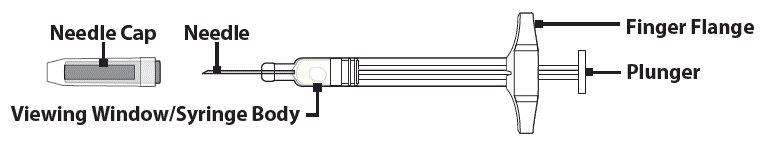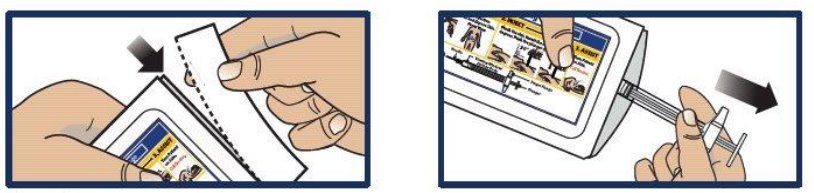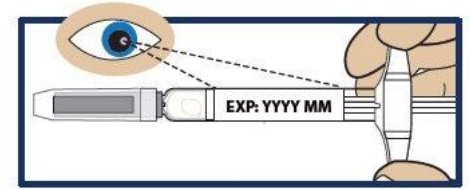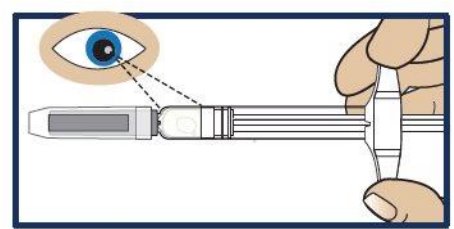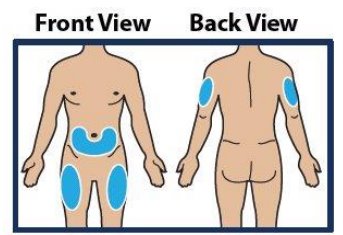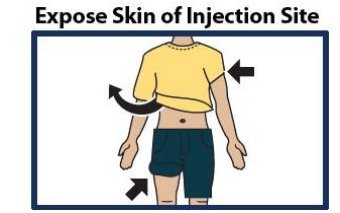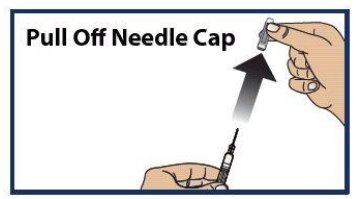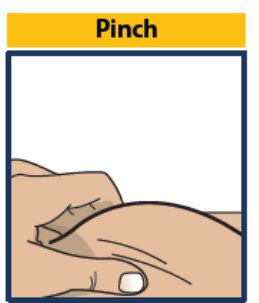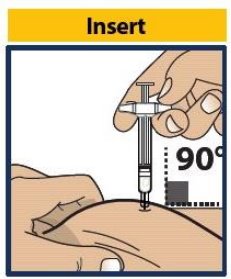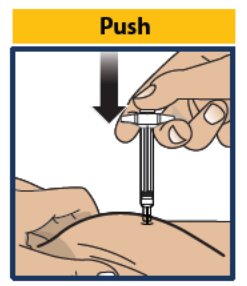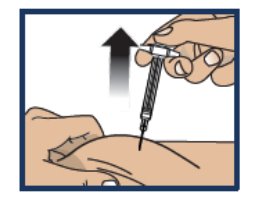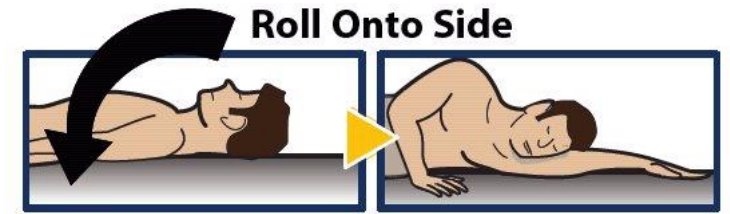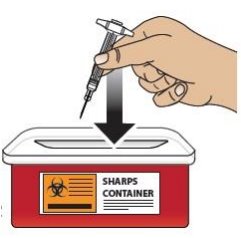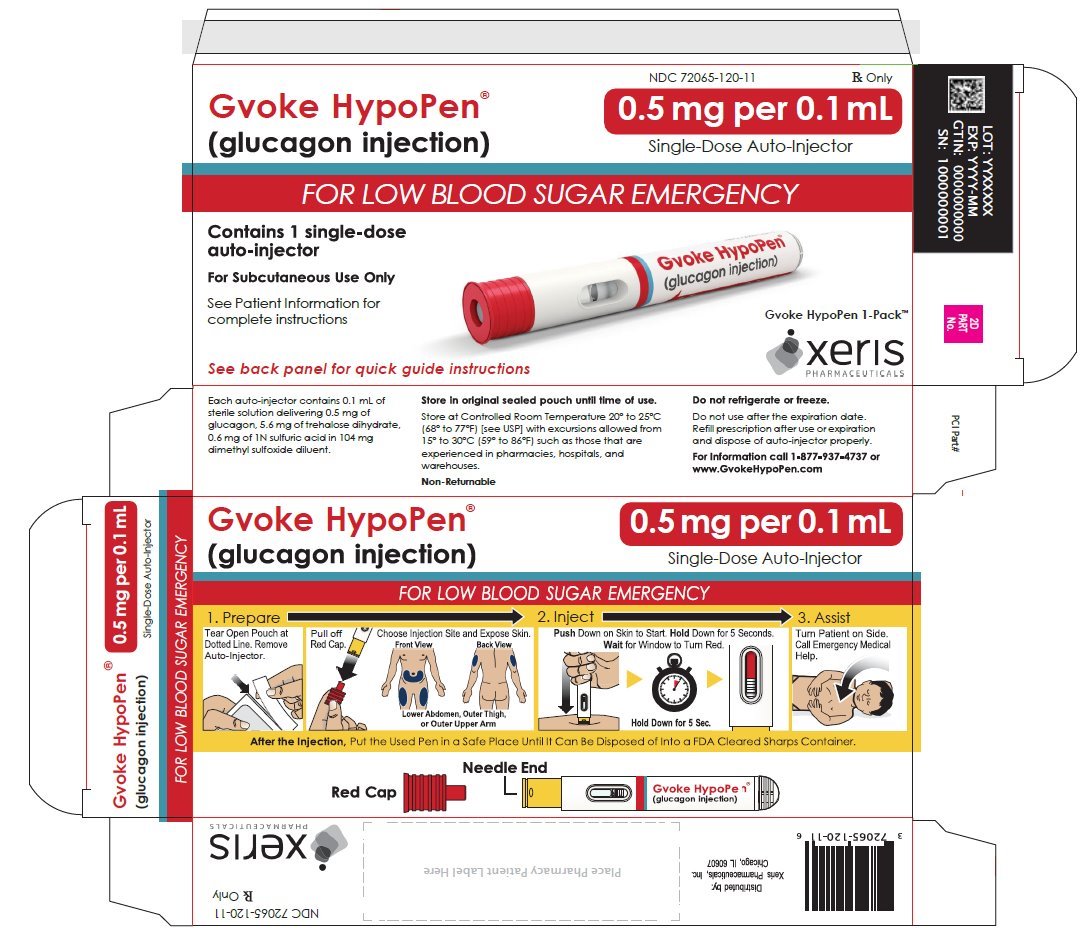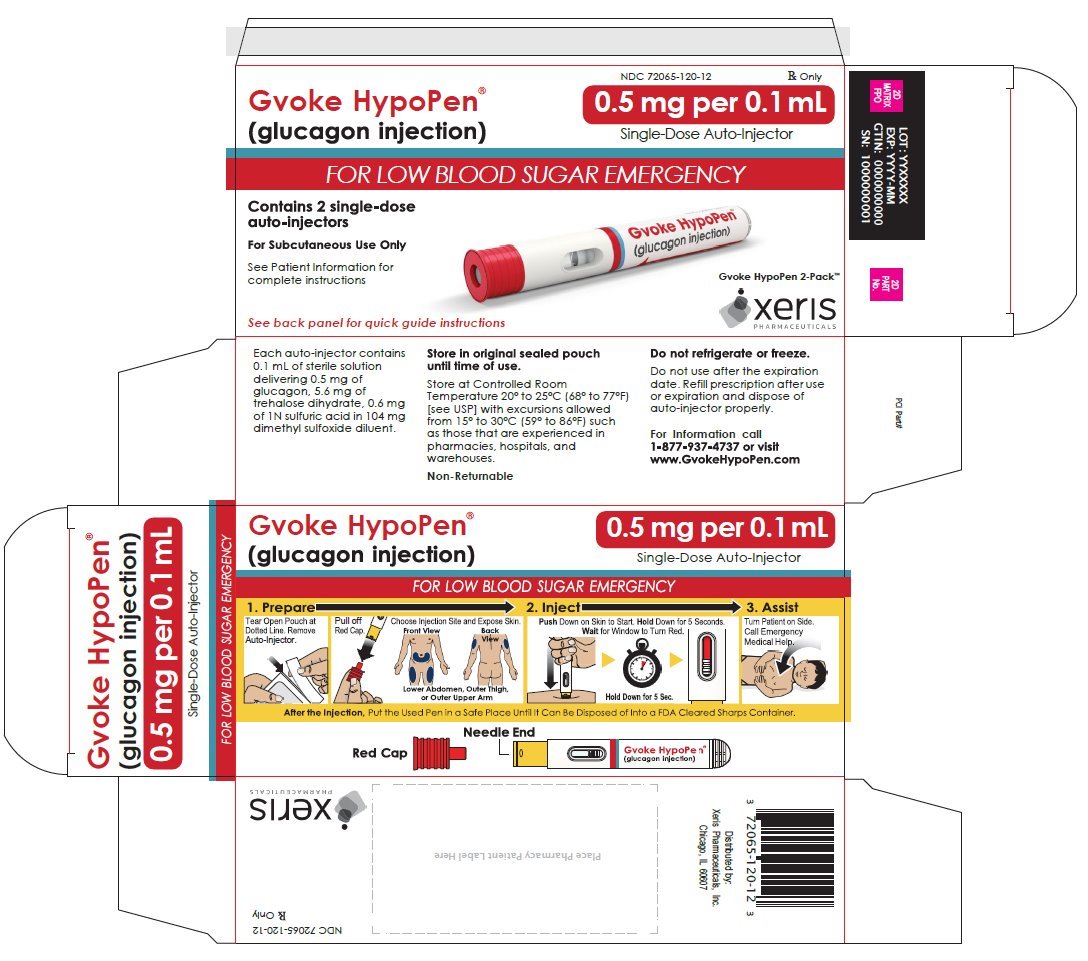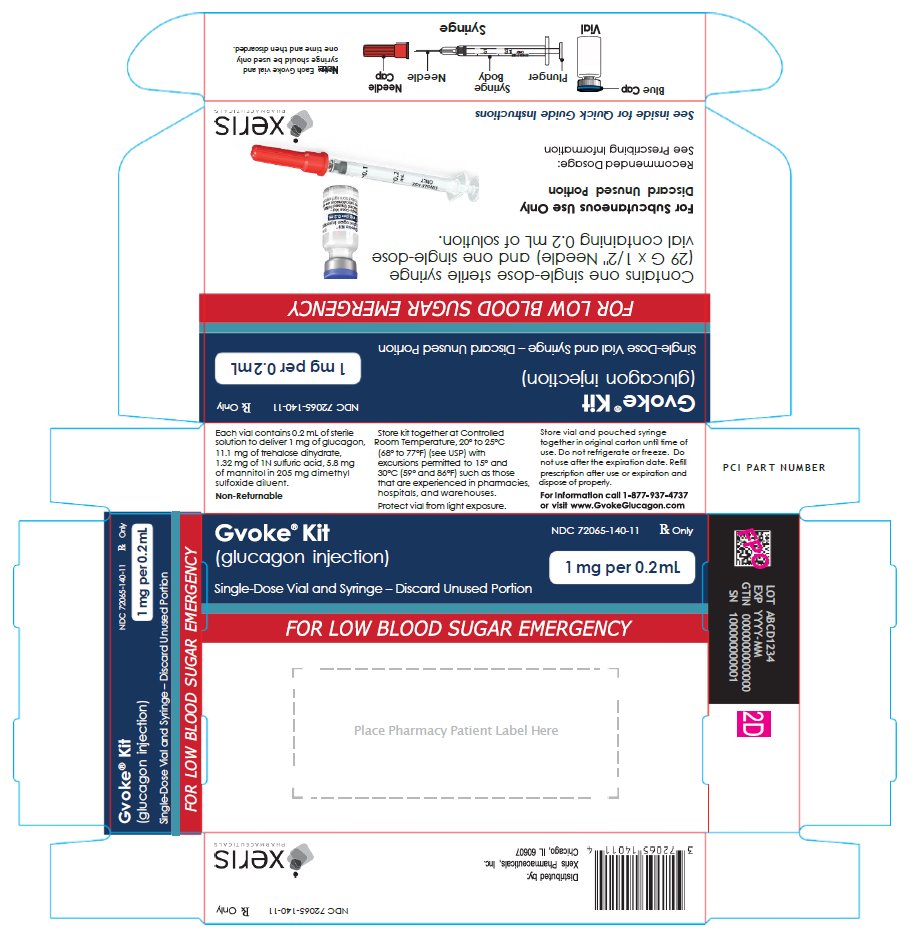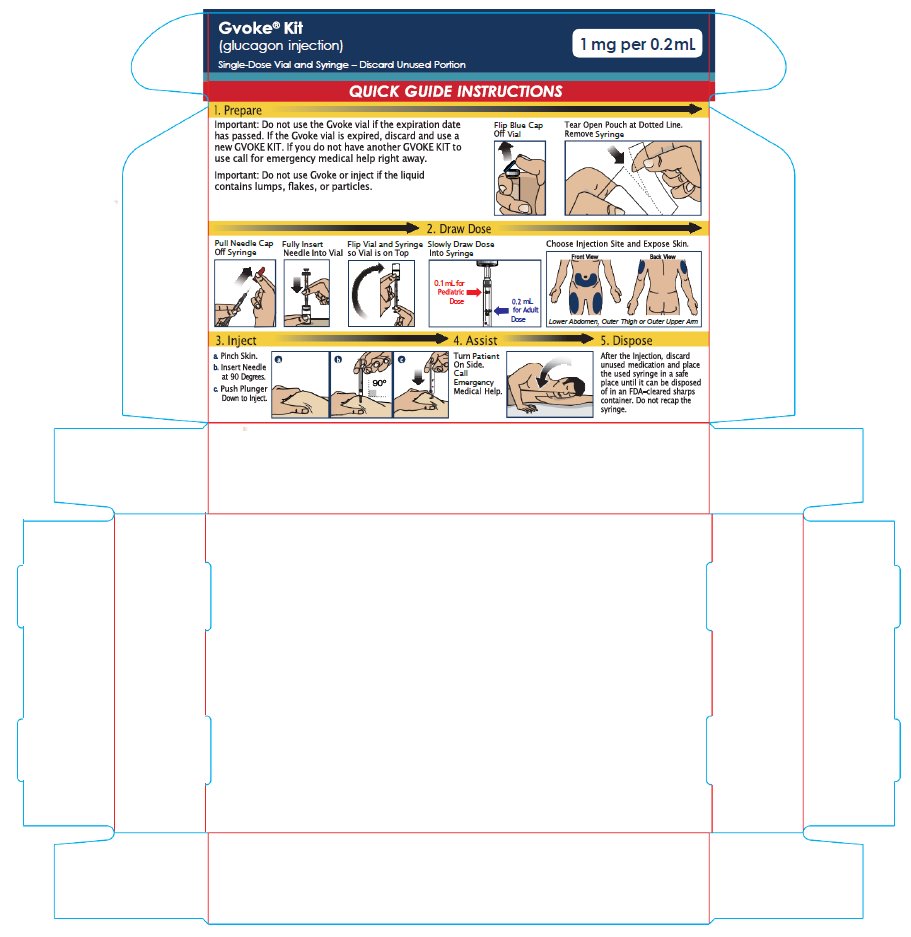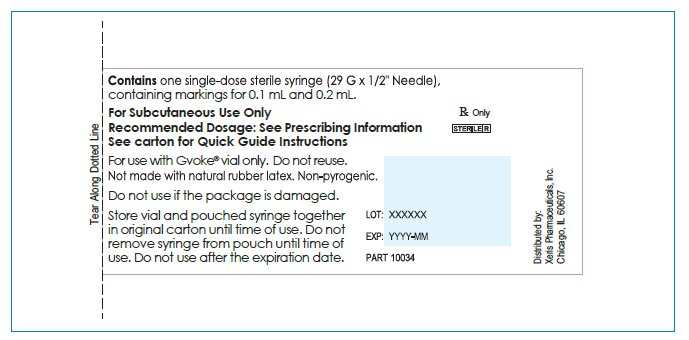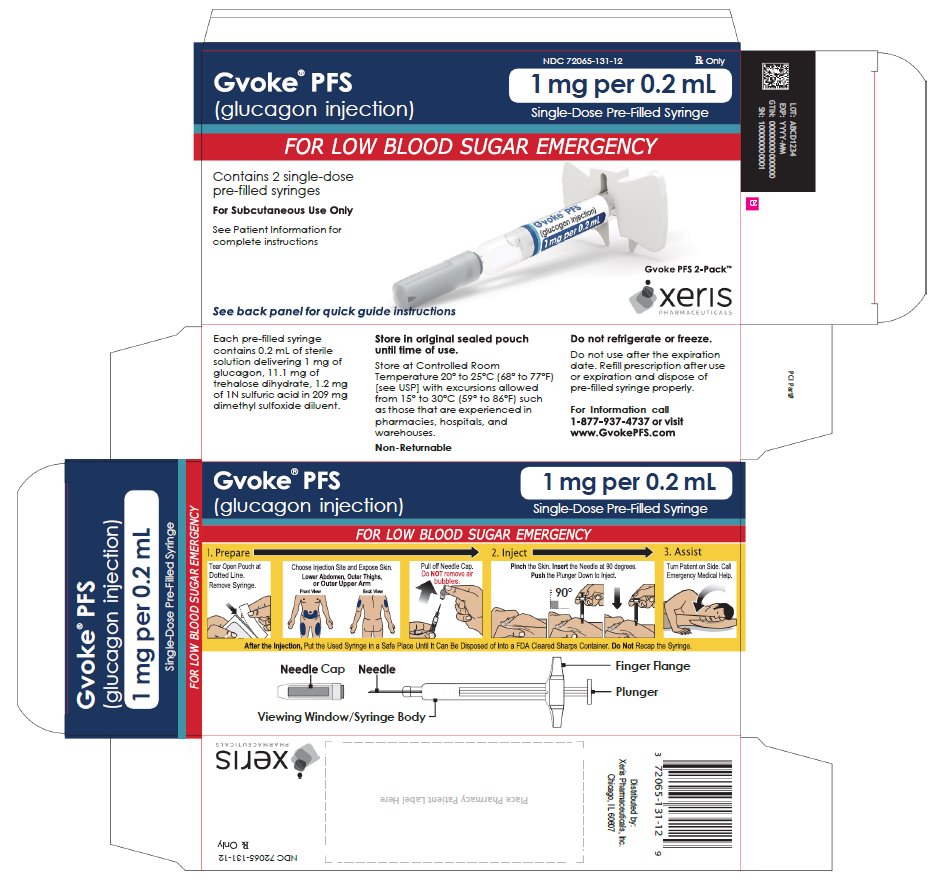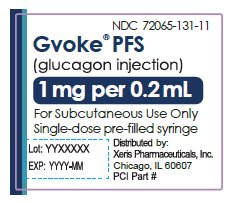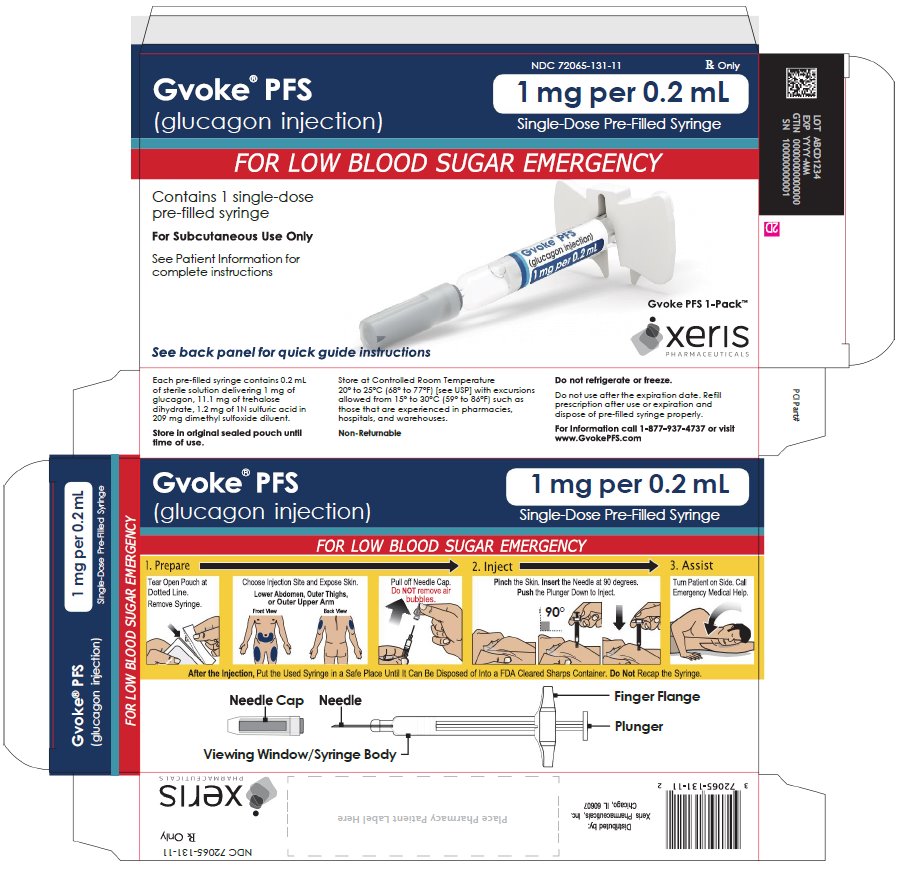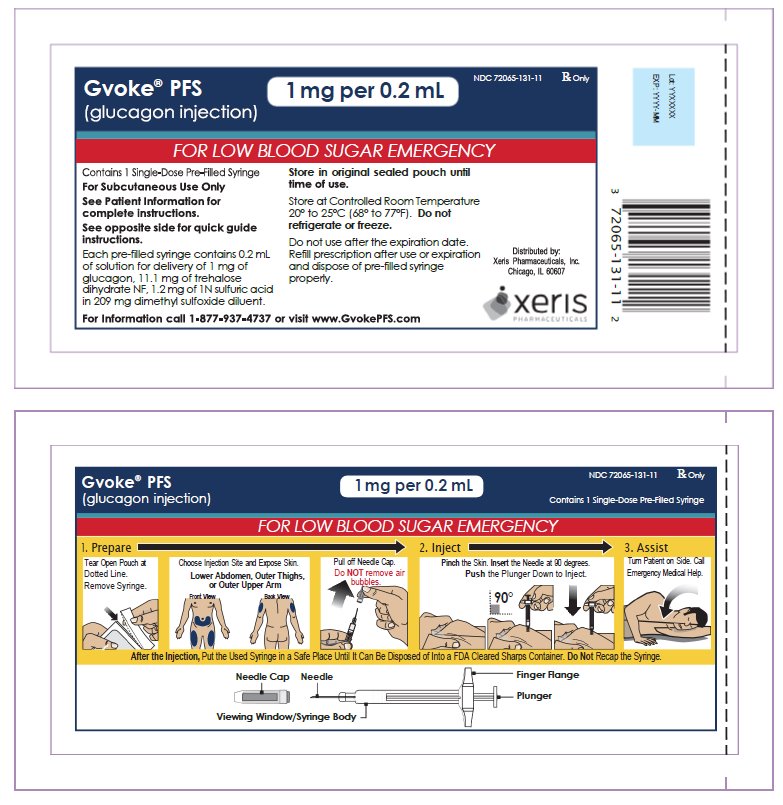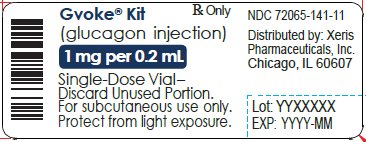 DRUG LABEL: Gvoke HypoPen
NDC: 72065-121 | Form: INJECTION, SOLUTION
Manufacturer: Xeris Pharmaceuticals, Inc.
Category: prescription | Type: HUMAN PRESCRIPTION DRUG LABEL
Date: 20251223

ACTIVE INGREDIENTS: GLUCAGON 1 mg/0.2 mL
INACTIVE INGREDIENTS: SULFURIC ACID; DIMETHYL SULFOXIDE

HIGHLIGHTS OF PRESCRIBING INFORMATION

These highlights do not include all the information needed to use GVOKE and GVOKE VialDx safely and effectively. See full prescribing information for GVOKE and GVOKE VialDx.
GVOKE (glucagon) injection, for subcutaneous use
GVOKE VialDx (glucagon) injection, for intravenous use
Initial U.S. Approval: 1960

RECENT MAJOR CHANGES

Indications and Usage (1.1, 1.2)
Dosage and Administration (2.1, 2.2)
Contraindications (4)
Warnings and Precautions (5.6, 5.7, 5.8)

03/2025

1 INDICATIONS AND USAGE

- GVOKE is an antihypoglycemic agent indicated for subcutaneous use for the treatment of severe hypoglycemia in adult and pediatric patients aged two years and older with diabetes (1.1)
- GVOKE VialDx is a gastrointestinal motility inhibitor indicated for intravenous use as a diagnostic aid during radiologic examinations to temporarily inhibit movement of the gastrointestinal tract in adult patients (1.2)

2 DOSAGE AND ADMINISTRATION

Dosage and Administration of GVOKE for Subcutaneous Use to Treat Severe Hypoglycemia in Adult and Pediatric Patients Aged 2 Years and Older with Diabetes (2.1)

- Important Administration Instructions
- Administer GVOKE HypoPen, GVOKE PFS, or GVOKE Kit subcutaneously. These three presentations are referred to as GVOKE in this labeling
- Administer GVOKE according to the printed instructions on the foil pouch label, carton, or the Instructions for Use.
- Visually inspect GVOKE prior to administration. The solution should appear clear and colorless to pale yellow.
- Administer GVOKE subcutaneously in the lower abdomen, outer thigh, or outer upper arm.
- Call for emergency assistance immediately after administering the dose.
- If there has been no response after 15 minutes, may administer an additional dose from a new HypoPen, GVOKE PFS, or GVOKE Kit while waiting for emergency assistance.
- When the patient has responded to GVOKE, give oral carbohydrates.
- Do not attempt to reuse GVOKE. Each GVOKE device or vial contains a single dose of glucagon. Do not reuse and discard any unused portion.
- Recommended Dosage
- Recommended dose for adult and pediatric patients aged 12 years of age and older is 1 mg.
- Recommended dose for adult and pediatric patients aged 12 years of age and older is 1 mg.
- The recommended dose for pediatric patients aged 2 to less than 12 years of age who weigh:
- Less than 45 kg, is 0.5 mg
- 45 kg or greater, is 1 mg

Dosage and Administration of GVOKE VialDx for Intravenous Use as a Diagnostic Aid in Adults (2.2)

- GVOKE VialDx is only for intravenous use under medical supervision.
- The recommended diagnostic dose for relaxation of the stomach, duodenal bulb, duodenum, and small bulb is 0.2 mg to 0.5 mg; the recommended dose to relax the colon is 0.5 mg to 0.75 mg.
- See the Full Prescribing Information for administration instructions for GVOKE VialDx.

3 DOSAGE FORMS AND STRENGTHS

Subcutaneous Injection:

- 0.5 mg/0.1 mL single-dose prefilled autoinjector (GVOKE HypoPen) (3)
- 1 mg/0.2 mL single-dose prefilled autoinjector (GVOKE HypoPen) (3)
- 1 mg/0.2 mL single-dose prefilled syringe (GVOKE PFS) (3)
- 1 mg/0.2 mL single-dose vial and syringe kit (GVOKE Kit)(3)

Intravenous Injection

- 1 mg/0.2 mL single-dose vial (GVOKE VialDx)(3)

4 CONTRAINDICATIONS

- Pheochromocytoma (4)
- Insulinoma (4)
- Prior hypersensitivity reaction to glucagon or to any of the excipients (4)
- Glucagonoma when used as a diagnostic aid (4)

5 WARNINGS AND PRECAUTIONS

- Substantial Increase in Blood Pressure in Patients with Pheochromocytoma: Contraindicated in patients with pheochromocytoma because glucagon may stimulate the release of catecholamines from the tumor. (5.1)
- Hypoglycemia in Patients with Insulinoma: In patients with insulinoma, administration may produce an initial increase in blood glucose; however, glucagon may stimulate exaggerated insulin release from an insulinoma and cause hypoglycemia. If a patient develops symptoms of hypoglycemia after a dose of GVOKE or GVOKE VialDx, give glucose orally or intravenously. (5.2)
- Serious Hypersensitivity Reactions: Serious hypersensitivity reactions have been reported with glucagon products, including generalized rash, and in some cases anaphylactic shock with breathing difficulties, and hypotension.(5.3)
- Lack of Efficacy with Subcutaneous Use for Severe Hypoglycemia in Patients with Decreased Hepatic Glycogen: Patients with insufficient hepatic stores of glycogen may not respond to GVOKE for subcutaneous use for the treatment of severe hypoglycemia. Insufficient hepatic stores of glycogen may be present in conditions such as states of starvation, or in patients with adrenal insufficiency or chronic hypoglycemia. (5.4)
- Necrolytic Migratory Erythema (NME): a skin rash, has been reported postmarketing following continuous glucagon infusion and resolved with discontinuation of the glucagon. GVOKE and GVOKE VialDx are not approved for continuous infusion. Should NME occur, consider whether the benefits of continuous glucagon infusion outweigh the risks. (5.5)
- Hyperglycemia with Intravenous Use as a Diagnostic Aid in Patients with Diabetes Mellitus: GVOKE VialDx in patients with diabetes mellitus may cause hyperglycemia. Monitor patients with diabetes for changes in blood glucose levels during treatment and treat hyperglycemia if indicated. (5.6)
- Blood Pressure and Heart Rate Increases with Intravenous Use as a Diagnostic Aid in Patients with Cardiac Disease: GVOKE VialDx may increase myocardial oxygen demand, blood pressure, and pulse rate. Cardiac monitoring is recommended in patients with cardiac disease during use of GVOKE VialDx as a diagnostic aid, and an increase in blood pressure and pulse rate may require therapy. (5.7)
- Hypoglycemia in Patients with Glucagonoma with Intravenous Use as a Diagnostic Aid: GVOKE VialDx administered to patients with glucagonoma may cause secondary hypoglycemia. Test patients suspected of having glucagonoma for blood levels of glucagon prior to treatment and monitor for changes in blood glucose levels during treatment. (5.8)

6 ADVERSE REACTIONS

- Most common adverse reactions (incidence 2% or greater) reported for GVOKE were:
  - Adults—nausea, vomiting, injection site edema raised 1 mm or greater, and headache (6.1)
  - Pediatric Patients—nausea, hypoglycemia, vomiting, headache, abdominal pain, hyperglycemia, injection site discomfort and reaction, and urticaria (6.1)
- Most common adverse reactions (incidence 5 % or greater) reported for GVOKE VialDx were nausea, dysgeusia, headache, dizziness and hot flush (6.1)

To report SUSPECTED ADVERSE REACTIONS, contact Xeris Pharmaceuticals, Inc. at toll-free 1-877-937-4737 or FDA at 1-800-FDA-1088 or www.fda.gov/medwatch

7 DRUG INTERACTIONS

- Beta-blockers: GVOKE- or GVOKE VialDx-treated patients taking concomitant beta-blockers may have a transient increase in pulse and blood pressure. (7)
- Indomethacin: In patients taking concomitant indomethacin, GVOKE may lose its ability to raise glucose or may produce hypoglycemia. (7)
- Anticholinergic drugs: Concomitant use of anticholinergic drugs with GVOKE VialDx for use as a diagnostic aid is not recommended. (7)
- Warfarin: GVOKE and GVOKE VialDx may increase the anticoagulant effect of warfarin. (7)
- Insulin: Monitor blood glucose when GVOKE VialDx is used as a diagnostic aid in patients receiving insulin. (7)

See 17 for PATIENT COUNSELING INFORMATION and FDA‑approved patient labeling for GVOKE.

FULL PRESCRIBING INFORMATION

1 INDICATIONS AND USAGE

1.1 Severe Hypoglycemia in Adult and Pediatric Patients Aged 2 Years and Older with Diabetes

GVOKE is indicated for subcutaneous use for the treatment of severe hypoglycemia in adult and pediatric patients aged two and older with diabetes.

1.2 Diagnostic Aid in Adults

GVOKE VialDx is indicated for intravenous use as a diagnostic aid during radiologic examinations to temporarily inhibit movement of the gastrointestinal tract in adult patients.

2 DOSAGE AND ADMINISTRATION

2.1 Dosage and Administration of GVOKE for Subcutaneous Use to Treat Severe Hypoglycemia in Adult and Pediatric Patients Aged 2 Years and Older with Diabetes

Important Administration Instructions

To treat severe hypoglycemia in adult and pediatric patients aged 2 years and older with diabetes, administer GVOKE HypoPen, GVOKE PFS, or GVOKE Kit subcutaneously. These three presentations are only for subcutaneous use and are referred to as GVOKE in this labeling.

- For GVOKE HypoPen or GVOKE PFS: Do not open foil pouch until ready to administer.
- For GVOKE Kit: Store in original carton until ready to administer.

Instruct patients and their caregivers on the signs and symptoms of severe hypoglycemia. Because severe hypoglycemia requires the help of others to recover, instruct the patient to inform those around them about GVOKE and its Instructions for Use. Administer GVOKE subcutaneously as soon as possible when severe hypoglycemia is recognized.

Instruct the patient or caregiver to read the Instructions for Use at the time they receive a prescription for GVOKE.

- Visually inspect GVOKE prior to administration. The solution should be clear, colorless to pale yellow
- Withdraw the correct dose (see below for dosage recommendations).
- Administer subcutaneously in the lower abdomen, outer thigh, or outer upper arm, according to the printed instructions on the foil pouch label, carton, or the Instructions for Use.
- Call for emergency assistance immediately after administering the dose.
- If there has been no response after 15 minutes, an additional dose from a new GVOKE HypoPen, GVOKE PFS, or GVOKE Kit may be administered while waiting for emergency assistance.
- When the patient has responded to GVOKE, give oral carbohydrates to restore the liver glycogen and prevent recurrence of hypoglycemia.
- Each GVOKE HypoPen, GVOKE PFS, or GVOKE Kit product contains a single dose of glucagon. Do not reuse and discard any unused portion.

Recommended Dosage in Adult and Pediatric Patients Aged 12 Years and Older to Treat Severe Hypoglycemia

To treat severe hypoglycemia in patients 12 years of age and older with diabetes, use GVOKE HypoPen, GVOKE PFS, or GVOKE Kit:

- The recommended dose is 1 mg administered by subcutaneous injection into lower abdomen, outer thigh, or outer upper arm.
- If there has been no response after 15 minutes, an additional 1 mg dose from a new GVOKE HypoPen, GVOKE PFS, or GVOKE Kit may be administered while waiting for emergency assistance

Recommended Dosage in Pediatric Patients Aged 2 to less than 12 Years of Age to Treat Severe Hypoglycemia

To treat severe hypoglycemia in pediatric patients aged 2 to less than 12 years of age with diabetes, use GVOKE HypoPen, GVOKE PFS, or GVOKE Kit.

- The recommended dose in those who weigh:
- Less than 45 kg is 0.5 mg administered by subcutaneous injection into the lower abdomen, outer thigh, or outer upper arm.
- 45 kg or greater is 1 mg administered by subcutaneous injection into the lower abdomen, outer thigh, or outer upper arm.
- If there has been no response after 15 minutes, an additional 0.5 mg dose (for those who weigh less than 45 kg) or 1 mg dose (for those who weigh 45 kg or greater) from a new GVOKE HypoPen, GVOKE PFS, or GVOKE Kit may be administered while waiting for emergency assistance.

2.2 Dosage and Administration of GVOKE VialDx for Intravenous Use as a Diagnostic Aid in Adults

Important Administration Information

For use as a diagnostic aid during radiologic examinations to temporarily inhibit movement of the gastrointestinal tract, use GVOKE VialDx. GVOKE VialDx is only for intravenous use under medical supervision

- Must be diluted with 0.9% Sodium Chloride Injection prior to administration. Using a syringe, draw 0.2 mL from the GVOKE VialDx vial and dispense into a separate empty sterile container containing 2 mL of 0.9% Sodium Chloride Injection.
- Gently swirl the container until the solution is thoroughly mixed. The mixed solution should be clear and colorless to pale yellow. Inspect visually for particulate matter and discoloration.
- The final concentration of the diluted solution is 0.45 mg/mL of glucagon. Draw the required dose from the container into a syringe for administration (see below for dosage recommendations).
- If not used immediately, diluted GVOKE VialDx may be stored for up to 8 hours after initial dilution.
- Inject the solution intravenously via a 1-minute slow push using consistent pressure.
- After the end of the diagnostic procedure, give oral carbohydrates to patients who have been fasting, if this is compatible with the diagnostic procedure.
- GVOKE VialDx contains a single dose of glucagon. Do not reuse. Discard any unused portion.

Recommended Dosage in Adults as a Diagnostic Aid

For use as a diagnostic aid during radiologic examinations to temporarily inhibit movement of the gastrointestinal tract, use GVOKE VialDx. The recommended intravenous dose for relaxation of the [see Clinical Pharmacology (12.2)]:

- Stomach, duodenal bulb, duodenum, and small bowel is 0.2 mg to 0.5 mg
- Colon is 0.5 mg to 0.75 mg

The onset of action after an injection will depend on the organ under examination [see Clinical Pharmacology (12.2)].

3 DOSAGE FORMS AND STRENGTHS

GVOKE HypoPen, GVOKE PFS, GVOKE Kit (these three presentations are also referred to as GVOKE in this labeling) , and GVOKE VialDx are clear, colorless to pale yellow solutions.

Subcutaneous Injection

- Injection: 0.5 mg/0.1 mL single-dose prefilled autoinjector (GVOKE HypoPen)
- Injection: 1 mg/0.2 mL single-dose prefilled autoinjector (GVOKE HypoPen)
- Injection: 1 mg/0.2 mL single-dose prefilled syringe (GVOKE PFS)
- Injection: 1 mg/0.2 mL single-dose vial and syringe kit (GVOKE Kit)

Intravenous Injection:

- Injection: 1 mg/0.2 mL single-dose vial (GVOKE VialDx)

4 CONTRAINDICATIONS

GVOKE and GVOKE VialDx are contraindicated in patients with:

- Pheochromocytoma because of the risk of substantial increase in blood pressure [see Warnings and Precautions (5.1)]
- Insulinoma because of the risk of hypoglycemia [see Warnings and Precautions (5.2)]
- Prior hypersensitivity reaction to glucagon or to any of the excipients in GVOKE or GVOKE VialDx. Serious hypersensitivity reactions have been reported with glucagon and include anaphylactic shock with breathing difficulties and hypotension [see Warnings and Precautions (5.3)].

GVOKE VialDx for use as a diagnostic aid is also contraindicated in patients with glucagonoma because of risk of hypoglycemia [see Warnings and Precautions (5.8)]

5 WARNINGS AND PRECAUTIONS

5.1 Substantial Increase in Blood Pressure in Patients with Pheochromocytoma

GVOKE and GVOKE VialDx are contraindicated in patients with pheochromocytoma because glucagon may stimulate the release of catecholamines from the tumor [see Contraindications (4)]. If the patient develops a substantial increase in blood pressure and a previously undiagnosed pheochromocytoma is suspected, 5 to 10 mg of phentolamine mesylate, administered intravenously, has been shown to be effective in lowering blood pressure.

5.2 Hypoglycemia in Patients with Insulinoma

In patients with insulinoma, administration of glucagon may produce an initial increase in blood glucose; however, glucagon administration may directly or indirectly (through an initial rise in blood glucose) stimulate exaggerated insulin release from an insulinoma and cause hypoglycemia. GVOKE and GVOKE VialDx are contraindicated in patients with insulinoma [see Contraindications (4)]. If a patient develops symptoms of hypoglycemia after a dose of GVOKE or GVOKE VialDx, give glucose orally or intravenously.

5.3 Serious Hypersensitivity Reactions

Serious hypersensitivity reactions have been reported with glucagon products, including generalized rash, and in some cases anaphylactic shock with breathing difficulties and hypotension. Discontinue GVOKE or GVOKE VialDx if symptoms of serious hypersensitivity reactions occur. Advise patients and/or caregivers to seek immediate medical attention if the patient experiences any symptoms of serious hypersensitivity reactions.GVOKE and GVOKE VialDx are contraindicated in patients with a prior hypersensitivity reaction to glucagon, or any of the excipients in GVOKE and GVOKE VialDx [see Contraindications (4)].

5.4 Lack of Efficacy with Subcutaneous Use for Severe Hypoglycemia in Patients with Decreased Hepatic Glycogen

Patients with insufficient hepatic stores of glycogen may not respond to GVOKE for the treatment of severe hypoglycemia [see Clinical Pharmacology (12.2)]. Insufficient hepatic stores of glycogen may be present in conditions such as states of starvation, or in patients with adrenal insufficiency or chronic hypoglycemia.

5.5 Necrolytic Migratory Erythema

Necrolytic migratory erythema (NME), a skin rash commonly associated with glucagonomas (glucagon-producing tumors) and characterized by scaly, pruritic erythematous plaques, bullae, and erosions, has been reported postmarketing following continuous glucagon infusion.GVOKE and GVOKE VialDx are not approved for continuous infusion. NME lesions may affect the face, groin, perineum and legs or be more widespread. In the reported cases NME resolved with discontinuation of the glucagon, and treatment with corticosteroids was not effective. Should NME occur, consider whether the benefits of continuous glucagon infusion outweigh the risks.

5.6 Hyperglycemia with Intravenous Use as a Diagnostic Aid in Patients with Diabetes Mellitus

GVOKE VialDx in patients with diabetes mellitus may cause hyperglycemia. Monitor patients with diabetes for changes in blood glucose levels during treatment with GVOKE VialDx and treat hyperglycemia, if indicated.

5.7 Blood Pressure and Heart Rate Increases with Intravenous Use as a Diagnostic Aid in Patients with Cardiac Disease

GVOKE VialDx may increase myocardial oxygen demand, blood pressure, and pulse rate which may be life threatening in patients with cardiac disease. Cardiac monitoring is recommended in patients with cardiac disease during use of GVOKE VialDx as a diagnostic aid, and an increase in blood pressure and pulse rate may require therapy.

5.8 Hypoglycemia in Patients with Glucagonoma with Intravenous Use as a Diagnostic Aid

Use of GVOKE VialDx in patients with glucagonoma may cause secondary hypoglycemia. GVOKE VialDx is contraindicated in patients with glucagonoma when used as a diagnostic aid [see Contraindications (4)]. Test patients suspected of having glucagonoma for blood levels of glucagon prior to administration of GVOKE VialDx, and monitor for changes in blood glucose levels during treatment. If a patient develops symptoms of hypoglycemia after administration of GVOKE VialDx, administer glucose orally or intravenously.

6 ADVERSE REACTIONS

The following serious adverse reactions are described below and elsewhere in labeling:

- Substantial Increase in Blood Pressure in Patients with Pheochromocytoma [see Warnings and Precautions (5.1)].
- Hypoglycemia in Patients with Insulinoma [see Warnings and Precautions (5.2)].
- Serious Hypersensitivity Reactions [see Warnings and Precautions (5.3)]
- Lack of Efficacy With Subcutaneous Use for Severe Hypoglycemia in Patients with Decreased Hepatic Glycogen [see Warnings and Precautions (5.4)]
- Necrolytic Migratory Erythema [see Warnings and Precautions (5.5)].
- Hyperglycemia with Intravenous Use as a Diagnostic Aid in Patients with Diabetes Mellitus [see Warnings and Precautions (5.6)]
- Blood Pressure and Heart Rate Increases with Intravenous Use as a Diagnostic Aid in Patients with Cardiac Disease [see Warnings and Precautions (5.7)]
- Hypoglycemia in Patients with Glucagonoma with Intravenous Use as a Diagnostic Aid [see Warnings and Precautions (5.8)]

6.1 Clinical Trials Experience

Because clinical trials are conducted under widely varying conditions, adverse reaction rates observed in the clinical trials of GVOKE and GVOKE VialDx cannot be directly compared to rates in the clinical trials of other drugs and may not reflect the rates observed in practice.

GVOKE for Subcutaneous Use for the Treatment of Severe Hypoglycemia in Adult and Pediatric Patients 2 Aged Years and Older with Type 1 Diabetes Mellitus

Adverse Reactions in Adult Patients

The safety of GVOKE for subcutaneous use for the treatment of severe hypoglycemia in adults with diabetes was evaluated in two randomized, blinded, 2-way crossover studies conducted in adults with type 1 diabetes mellitus. In total, 154 patients received a subcutaneous injection of GVOKE [see Clinical Studies (14.1)].

The most common adverse reactions that occurred in 2% or more of adults treated with GVOKE during these two clinical trials are listed in Table 1.

Table 1: Adverse Reactions that occurred ≥ 2% in Adult Patients with Type 1 Diabetes Mellitus Treated with GVOKEa
 | GVOKE 1 mg dose; (N = 154)
Nausea | 30%
Vomiting | 16%
Injection site edema raised 1 mm or greater | 7%
Headache | 5%
aAdverse Reactions that occurred within 12 hours.

Injection site pain was reported by 1% of GVOKE-treated patients.

Hypertension and tachycardia have occurred with glucagon treatment.

Adverse Reactions in Pediatric Patients Aged 2 Years and Older

The safety of GVOKE for the treatment of severe hypoglycemia in patients with diabetes was evaluated in one single-arm, open-label, study in 31 pediatric patients with type 1 diabetes mellitus [see Clinical Studies (14.2)].

The data in Table 2 reflect the exposure of 31 pediatric patients to 0.5 mg or 1 mg of GVOKE given subcutaneously. The most common adverse reactions that occurred in ≥2% of GVOKE-treated pediatric patients aged 2 years and older are listed in Table 2.

Table 2: Adverse Reactions That Occurred ≥ 2% in GVOKE-treated Pediatric Patients Aged 2 Years and Older with Type 1 Diabetes Mellitusa
 | 2 to 6 years of age (0.5 mg dose) N =7 | 6 to 12 years of age (0.5 mg dose) N = 13 | 12 to 18 years of age (1 mg dose) N = 11 | Total N = 31
Nausea | 43% | 54% | 36% | 45%
Hypoglycemia | 29% | 54% | 27% | 39%
Vomiting | 14% | 23% | 18% | 19%
Headache | 0% | 15% | 0% | 7%
Abdominal pain | 0% | 8% | 0% | 3%
Hyperglycemia | 14% | 8% | 0% | 7%
Injection site discomfort | 0% | 8% | 0% | 3%
Injection site reaction | 0% | 0% | 9% | 3%
Urticaria | 0% | 8% | 0% | 3%
aAdverse Reactions that occurred within 12 hours.

GVOKE VialDx for Intravenous Use As a Diagnostic Aid in Adults
The safety of GVOKE VialDx for intravenous use as a diagnostic aid in adults was evaluated in an open-label single-dose study in 83 adult healthy volunteers. Table 3 displays the most common adverse reactions that occurred in 5% or greater in healthy volunteers who received 0.75 mg of GVOKE VialDx intravenously.

Table 3: Adverse Reactions that Occurred ≥ 5 % in Adult Healthy Volunteers Who Received 0.75 mg of GVOKE VialDx for Intravenous Use as a Diagnostic Aid
 | N=83
Nausea | 37.3%
Dysgeusia | 18.1%
Headache | 10.8%
Hot Flush | 9.6%
Dizziness | 8.4%

6.2 Postmarketing Experience

Additional adverse reactions have been identified during post-approval use of glucagon. Because these reactions are reported voluntarily from a population of uncertain size, it is generally not possible to reliably estimate their frequency or establish a causal relationship to drug exposure.

- Necrolytic migratory erythema (NME) cases have been reported postmarketing in patients receiving continuous infusion of glucagon.
- Hypoglycemia and hypoglycemic coma. Patients taking indomethacin may be more likely to experience hypoglycemia following glucagon administration [see Drug Interactions (7)].

7 DRUG INTERACTIONS

Table 4: Clinically Significant Drug Interaction with GVOKE and GVOKE VialDx
Beta-Blockers
Clincial Impact: | Patients taking beta-blockers may have a transient increase in pulse and blood pressure when given GVOKE or GVOKE VialDx.
Intervention | The increase in blood pressure and heart rate may require therapy in patients with coronary artery disease.
Insulin
Clincial Impact: | Insulin acts antagonistically to glucagon.
Intervention | Monitor blood glucose when GVOKE VialDx is used as a diagnostic aid in patients receiving insulin.
Indomethacin
Clincial Impact: | In patients taking indomethacin, GVOKE may lose its ability to raise blood glucose or may even produce hypoglycemia.
Intervention | Monitor blood glucose levels during glucagon treatment of patients taking indomethacin.
Anticholinergic Drugs
Clincial Impact: | The concomitant use of anticholinergic drugs and GVOKE VialDx increases the risk of gastrointestinal adverse reactions due to additive effects on inhibition of gastrointestinal motility.
Intervention | Concomitant use of anticholinergic drugs with GVOKE VialDx is not recommended.
Warfarin
Clincial Impact: | GVOKE and GVOKE Vial Dx may increase the anticoagulant effect of warfarin.
Intervention | Monitor patients for unusual bruising or bleeding, as adjustments in warfarin dosage may be required.

8 USE IN SPECIFIC POPULATIONS

8.1 Pregnancy

Risk Summary

Available data from case reports and a small number of observational studies with glucagon use in pregnant women over decades of use have not identified a drug-associated risk of major birth defects, miscarriage or adverse maternal or fetal outcomes. Multiple small studies have demonstrated a lack of transfer of pancreatic glucagon across the human placental barrier during early gestation. In a rat reproduction study, no embryofetal toxicity was observed with glucagon administered by injection during the period of organogenesis at doses representing up to 40 times the human dose, based on body surface area (mg/m^2) (see Data).

The estimated background risk of major birth defects and miscarriage for the indicated population is unknown. In the U.S. general population, the estimated background risk of major birth defects and miscarriage in clinically recognized pregnancies is 2-4% and 15-20%, respectively.

Data

Animal Data

In pregnant rats given animal sourced glucagon twice-daily by injection at doses up to 2 mg/kg (up to 40 times the human dose based on body surface area extrapolation, mg/m^2) during the period of organogenesis, there was no evidence of increased malformations or embryofetal lethality.

8.2 Lactation

Risk Summary

There is no information available on the presence of glucagon in human or animal milk, the effects of the drug on the breastfed infant, or the effects of the drug on milk production. However, glucagon is a peptide and would be expected to be broken down to its constituent amino acids in the infant's digestive tract and is therefore, unlikely to cause harm to an exposed infant.

8.4 Pediatric Use

The safety and effectiveness of GVOKE for subcutaneous use for the treatment of severe hypoglycemia in patients with diabetes have been established in pediatric patients aged 2 years and older. Use of GVOKE for this indication is supported by evidence from two adequate and well-controlled studies in adults with type-1 diabetes mellitus [see Clinical Studies (14.1)] and from a study in 31 pediatric patients ages 2 and older with type 1 diabetes mellitus [see Clinical Studies (14.2)].

The safety and effectiveness of GVOKE for subcutaneous use for the treatment of severe hypoglycemia in patients with diabetes have not been established in pediatric patients younger than 2 years of age.

Safety and effectiveness of GVOKE VialDx for intravenous use as a diagnostic aid during radiologic examinations to temporarily inhibit movement of the gastrointestinal tract in pediatric patients have not been established.

8.5 Geriatric Use

Clinical studies of GVOKE and GVOKE VialDx did not include sufficient numbers of patients aged 65 and over to determine whether they respond differently from younger adult patients.

10 OVERDOSAGE

If overdosage occurs, the patient may experience nausea, vomiting, inhibition of GI tract motility, increase in blood pressure, and pulse rate. In case of suspected overdosing, serum potassium may decrease and should be monitored and corrected if needed. If the patient develops a dramatic increase in blood pressure, phentolamine mesylate has been shown to be effective in lowering blood pressure for the short time that control would be needed. In the event of an overdose of GVOKE, consider contacting the Poison Help line (1-800-222-1222) or a medical toxicologist for additional overdosage management recommendation.

11 DESCRIPTION

Glucagon is an antihypoglycemic agent and a gastrointestinal motility inhibitor. Glucagon is a single chain containing 29 amino acid residues and has a molecular weight of 3483 and is identical to human glucagon. Glucagon is of synthetic origin produced by solid phase synthesis.

Its molecular formula is C153H225N43O49S with the following structure:

GVOKE HypoPen, GVOKE PFS, and GVOKE Kit

GVOKE HypoPen (glucagon) injection, GVOKE PFS (glucagon) injection, and GVOKE Kit (glucagon) injection (these three presentations are also referred to as GVOKE (glucagon) injection in this labeling) are clear, colorless to pale yellow, sterile solutions for subcutaneous injection.

- GVOKE HypoPen and GVOKE PFS: Each 0.2 mL contains 1 mg of glucagon, 11.1 mg of trehalose dihydrate NF, and 1.2 mg of 1N sulfuric acid in 209 mg dimethyl sulfoxide diluent.
- GVOKE HypoPen: Each 0.1 mL contains 0.5 mg of glucagon, 5.6 mg of trehalose dihydrate NF, and 0.6 mg of 1N sulfuric acid in 104 mg dimethyl sulfoxide diluent.
- GVOKE Kit: Each 0.2 mL contains 1 mg of glucagon, 11.1 mg of trehalose dihydrate NF, 5.8 mg of mannitol USP, and 1.32 mg of 1N sulfuric acid in 205 mg dimethyl sulfoxide diluent.

GVOKE VialDx

GVOKE VialDx (glucagon) injection is a clear, colorless to pale yellow, sterile solution for intravenous injection available in 1 mg per 0.2 mL vial.

Each 0.2 mL of GVOKE VialDx contains 1 mg of glucagon, 11.1 mg of trehalose dihydrate NF, 5.8 mg of mannitol USP, and 1.32 mg of 1N sulfuric acid in 205 mg dimethyl sulfoxide diluent prior to dilution with 0.9% Sodium Chloride [for dilution instructions, see Dosage and Administration (2.2)].

The diluted solution contains 0.45 mg per mL glucagon, 5 mg per mL trehalose dihydrate, 93.2 mg per mL dimethyl sulfoxide, 2.6 mg per mL mannitol, and 0.60 mg per mL 1 N sulfuric acid.

12 CLINICAL PHARMACOLOGY

12.1 Mechanism of Action

Glucagon increases blood glucose concentration by activating hepatic glucagon receptors, thereby stimulating glycogen breakdown and release of glucose from the liver. Hepatic stores of glycogen are necessary for glucagon to produce an antihypoglycemic effect. Extrahepatic effects of glucagon include relaxation of the smooth muscle of the stomach, duodenum, small bowel, and colon.

12.2 Pharmacodynamics

GVOKE for Subcutaneous Use for the Treatment of Severe Hypoglycemia in Patients with Type 1 Diabetes Mellitus:

After subcutaneous administration of 1 mg GVOKE in adult patients with type 1 diabetes, the mean maximum glucose increase from baseline was 176 mg/dL (see Figure 1).

Plasma Glucose (mean ± standard error of the mean) vs. Time After Subcutaneous Administration of 1 mg of GVOKE in Adult Patients with Type 1 Diabetes Mellitus

In pediatric patients with type 1 diabetes mellitus (2 to less than 18 years), the mean maximum glucose increase from baseline was 134 mg/dL (2 to less than 6 years), 145 mg/dL (6 to less than 12 years), and 123 mg/dL (12 to less than 18 years) (see Figure 2).

Figure 2: Plasma Glucose (mean ± standard error of the mean) vs. Time After Subcutaneous Administration of GVOKE in Pediatric Patients with Type 1 Diabetes Mellitus

GVOKE VialDx Table 5 presents the pharmacodynamic properties of another glucagon product after intravenous administration

Table 5: Pharmacodynamic Properties of Another Glucagon Product After Intravenous Administration
Route of Administration | Dosea | Time of Maximal Glucose Concentration | Time of Onset of Action for GI Smooth Muscle Relaxation | Duration of Smooth Muscle Relaxation
Intravenous | 0.25 to 0.5 mg | 5 to 20 minutes | 45 seconds | 9 to 17 minutes
aDose is determined based on the length of the procedure

12.3 Pharmacokinetics

Absorption

Subcutaneous injection of 1 mg GVOKE in adult type 1 diabetes mellitus patients resulted in a mean glucagon Cmax of 2481.3 pg/mL, tmax of 50 minutes and AUC0‑240min of 3454.6 pg*min/mL.See Figure 3.

Figure 3: : Plasma Glucagon Concentration (mean ± standard error of the mean) vs. Time After Subcutaneous Administration of 1 mg of GVOKE in Adults with Type 1 Diabetes Mellitus

Distribution

The apparent volume of distribution was in the range of 137-2425 L.

Elimination

The half-life of GVOKE was determined to be 32 minutes.

Metabolism

Glucagon is extensively degraded in liver, kidney, and plasma.

Excretion

Urinary excretion of intact glucagon has not been measured.

Specific Populations

Pediatrics

Subcutaneous injection of 0.5 mg GVOKE in patients with type 1 diabetes mellitus ages 2 to under 6 years resulted in a mean glucagon Cmax of 2300 pg/mL, tmax of 41 minutes, and AUC0‑180min of 138900 pg/mL*min. Subcutaneous injection of 0.5 mg GVOKE in patients with type 1 diabetes ages 6 to under 12 years resulted in a mean Cmax of 1600 pg/mL, median tmax of 34 minutes and AUC0‑180min of 104700 pg/mL*min. Subcutaneous injection of 1 mg GVOKE in patients with type 1 diabetes ages 12 to less than 18 years resulted in a mean Cmax of 1900 pg/mL, tmax of 51 minutes AUC0‑180min of 134300 pg/mL*min. Mean plasma glucagon levels were similar across the age groups following age appropriate doses of GVOKE. See Figure 4.

Figure 4: Plasma Glucagon Concentration (mean ± standard error of the mean) vs. Time After Subcutaneous Administration of GVOKE in Pediatric Patients with Type 1 Diabetes Mellitus

13 NONCLINICAL TOXICOLOGY

13.1 Carcinogenesis, Mutagenesis, Impairment of Fertility

Long term studies in animals to evaluate carcinogenic potential have not been performed. Recombinant glucagon was positive in the bacterial Ames assay. It was determined that an increase in colony counts was related to technical difficulties in running this assay with peptides. Studies in rats have shown that glucagon does not cause impaired fertility.

14 CLINICAL STUDIES

14.1 Adult Patients with Type 1 Diabetes Mellitus for the Treatment of Severe Hypoglycemia

GVOKE was evaluated in adult patients aged 18 to 74 years with type 1 diabetes mellitus in two multi-center 2-way crossover studies: Study A was double-blinded with 80 patients, and Study B was single-blinded with 81 patients. Both studies involved 2 clinic visits 7 to 28 days apart, with random assignment to receive GVOKE 1 mg subcutaneous injection during one session and glucagon 1 mg subcutaneous injection (subcutaneous glucagon) during the other. In these studies, 154 patients received GVOKE and 157 patients received subcutaneous glucagon. A total of 152 patients received both GVOKE and subcutaneous glucagon.

The efficacy of GVOKE was compared to subcutaneous glucagon in patients who were in a state of insulin- induced hypoglycemia via insulin infusion with target plasma glucose less than 50 mg/dL. In Study A, mean plasma glucose at time of glucagon administration was 44.8 mg/dL and 45.2 mg/dL for the GVOKE and subcutaneous glucagon groups, respectively. In Study B, mean plasma glucose at time of glucagon administration was 47.7 mg/dL and 48.7 mg/dL for the GVOKE and subcutaneous glucagon groups, respectively.

Treatment “success” was defined as plasma glucose increase from mean value at time of glucagon administration to absolute value greater than 70 mg/dL or relative increase of 20 mg/dL or greater, at 30 minutes after glucagon administration. In a pooled analysis of Study A and Study B, the proportion of patients who achieved treatment “success” was 98.7 % in the GVOKE group and 100% in the subcutaneous glucagon group and the comparison between groups met the pre-specified non-inferiority margin. A summary of treatment “success” rates is shown in Table 6.

The mean time to treatment "success" was 13.8 minutes in the GVOKE group and 10 minutes the subcutaneous glucagon group.

Table 6:Adult Patients with Type 1 Diabetes Mellitus Treatment “Success” in Studies A and B
 | Study A (n=80) |  | Study B (n=81)
 | GVOKE | subcutaneous glucagon | GVOKE | subcutaneous glucagon
Treatment Success-n (%)a | 76 (97 %) | 79 (100%) | 76 (100%) | 78 (100%)
Glucose criteria met- n (%)
Greater than 70 mg/dL | 74 (95%) | 79 (100%) | 76 (100%) | 78 (100%)
20 mg/dL or greater increase from baseline | 76 (97%) | 79 (100%) | 76 (100%) | 78 (100%)
a Treatment success was defined as blood glucose greater than 70 mg/dL or an increase of blood glucose by 20 mg/dL or greater from baseline. The efficacy analysis population consisted of all patients who received both doses of the study drug.
b Percentage based on number of patients from both studies.

14.2 Pediatric Patients Aged 2 Years and Older with Type 1 Diabetes Mellitus for the Treatment of Severe Hypoglycemia

GVOKE was evaluated in a study in 31 pediatric patients with type 1 diabetes mellitus. Pediatric patients were administered insulin to induce a plasma glucose of less than 80 mg/dL, following which patients ages 2 to under 12 years of age received a 0.5 mg subcutaneous dose of GVOKE and patients ages 12 and older received a 0.5 mg or 1 mg subcutaneous dose of GVOKE.

All evaluable pediatric patients (30/30) achieved a target glucose increase of at least 25 mg/dL. Following administration, plasma glucose levels over time showed similar glucose responses for patients in each age group. A summary of plasma glucose results are shown in Table 7.

Table 7: Pediatric Patients with Type 1 Diabetes Mellitus Plasma Glucose by Age Group
Age Group | GVOKE Dose | Plasma Glucose (mg/dL); Mean (SD)
Age Group | GVOKE Dose | Baseline | 30 minutes | Change
2 to under 6 years (n=7) | 0.5 mg | 68.1 (8.3) | 149.6 (15.2) | 81.4 (18.3)
6 to under 12 years (n=13) | 0.5 mg | 71.6 (7.6) | 155.8 (26.5) | 84.2 (25.3)
12 to under 18 years (n=11) | 0.5 mg | 75.2(2.1) | 128.1(20.46) | 52.9(19.88)
12 to under 18 years (n=11) | 1 mg | 74.5(4.84) | 129.5 (29.5) | 55 (27.3)
SD=standard deviation

16 HOW SUPPLIED/STORAGE AND HANDLING

GVOKE glucagon injection is supplied as a clear, colorless to pale yellow solution in the following configurations:

Strength | Package Size | NDC number
For Subcutaneous Use
0.5 mg per 0.1 mL | 1 single-dose Gvoke HypoPen auto-injector | 72065-120-11
0.5 mg per 0.1 mL | 2 single-dose Gvoke HypoPen auto-injectors | 72065-120-12
1 mg per 0.2 mL | 1 single-dose Gvoke HypoPen auto-injector | 72065-121-11
1 mg per 0.2 mL | 2 single-dose Gvoke HypoPen auto-injectors (HypoPen) | 72065-121-12
1 mg per 0.2 mL | 1 single-dose GVOKE PFS pre-filled syringe | 72065-131-11
1 mg per 0.2 mL | 2 single-dose GVOKE PFS pre-filled syringes | 72065-131-12
1 mg per 0.2 mL | 1 single-dose GVOKE Kit vial and syringe kit | 72065-140-11
For Intravaneous Use
1 mg per 0.2 mL | 1 single-dose GVOKE VialDx vial | 0517-2901-01
1 mg per 0.2 mL | 10 single-dose GVOKE VialDx vials | 0517-2901-10

Store GVOKE HypoPen, GVOKE PFS, and GVOKE Kit (these three presentations are referred to as GVOKE in this labeling), and GVOKE VialDx at 20°C to 25°C (68°F to 77°F); excursions permitted between 15°C and 30°C (59°F and 86°F). Do not refrigerate or freeze. Do not expose to extreme temperatures.

- Store the GVOKE HypoPen and GVOKE PFS in the original sealed foil pouch until time of use
- Store the GVOKE Kit vial and pouched syringe together in original carton until time of use.
- Store GVOKE VialDx vials in original carton until time of use. Discard any unused portion

17 PATIENT COUNSELING INFORMATION

Advise the patient and family members or caregivers to read the GVOKE FDA-approved patient labeling (Patient Information and Instructions for Use).

Recognition of Severe Hypoglycemia

Inform patients with diabetes mellitus and family members or caregivers on how to recognize the signs and symptoms of severe hypoglycemia and the risks of prolonged hypoglycemia.

Serious Hypersensitivity Reactions

Inform patients that serious hypersensitivity reactions can occur with GVOKE and GVOKE VialDx. Advise patients to seek immediate medical attention if they experience any symptoms of serious hypersensitivity reactions [see Warnings and Precautions (5.3)].

Hyperglycemia with Intravenous Use as a Diagnostic Aid in Patients with Diabetes Mellitus

Inform patients with diabetes mellitus that treatment with GVOKE VialDx may increase their risk of hyperglycemia [see Warnings and Precautions (5.6)].

Blood Pressure and Heart Rate Increase with Intravenous Use as a Diagnostic Aid in Patients with Cardiac Disease

Inform patients with cardiac disease that intravenous treatment with GVOKE VialDx may increase their risk of a transient increase in blood pressure and heart rate [see Warnings and Precautions (5.7)].

GVOKE® is a trademark of Xeris Pharmaceuticals, Inc.

GVOKE is distributed by Xeris Pharmaceuticals, Inc.

For information contact:

Xeris Pharmaceuticals, Inc.

1375 W Fulton St., Suite 1300, Chicago IL 60607

1-877-XERIS-37 (1-877-937-4737)

https://www.xerispharma.com/www.xerispharma.com

© 2025 Xeris Pharmaceuticals, Inc.

GVOKE VialDxTM is distributed by:
American Reagent, Inc.
Shirley, NY 11967

INSTRUCTIONS FOR USE

GVOKE HypoPen®
[GEE-voke hypo-pen]
(glucagon injection)
Auto-injector
for subcutaneous use

This “Instructions for Use” contains information on how to inject GVOKE HypoPen®

Section headings and other template-related items found in this IFU are for organization of the document only and are not intended for use in corresponding artwork/patient-facing IFU files. Figure numbers in this content document may not correspond to figure numbers in corresponding artwork/patient-facing IFU files.

Appropriate trademark symbol (™ or ®) should be used upon first use of a trademarked name on each page; usage may differ from this content file and final artwork based on page layout.

1. GVOKE HYPOPEN® VISUAL

Understanding GVOKE HypoPen

Adult GVOKE HypoPen contains a 1 mg dose of glucagon and is in a foil pouch. Below is a picture of the pouch. See the GVOKE HypoPen package for a full view of the Quick-Use Guide.

Adult GVOKE HypoPen (1 mg dose)

Pediatric GVOKE HypoPen contains a 0.5 mg dose of glucagon and is in a foil pouch. Below is a picture of the pouch. See the GVOKE HypoPen package for a full view of the Quick-use guide.

Pediatric GVOKE HypoPen (0.5 mg dose)

HypoPen Device

Note: GVOKE HypoPen should be used one time and then thrown away (discarded)

2. IMPORTANT INFORMATION YOU NEED TO KNOW BEFORE INJECTING GVOKE HYPOPEN®

- Become familiar with the following instructions before an emergency happens.
- Do not use this auto-injector past the expiration date printed on the device. Replace GVOKE HypoPen before the expiration date on the box.
- If you have questions regarding the use of this product, talk to a healthcare provider or pharmacist.

Make sure that relatives, close friends, or caregivers know that if you become unconscious, they should call for emergency medical help right away. GVOKE HypoPen may have been prescribed so that relatives, close friends, and caregivers can give the injection if you become hypoglycemic (severe low blood sugar) and are unable to take sugar by mouth. If you are unconscious, GVOKE HypoPen can be given while awaiting medical assistance.

Show your relatives, close friends, or caregivers where you store GVOKE HypoPen and how to use it. They need to know how to use GVOKE HypoPen before an emergency situation happens.

Indications for Use

GVOKE HypoPen is for the treatment of severe hypoglycemia in pediatric and adult patients with diabetes ages 2 years and above. Symptoms of severe hypoglycemia include, unconsciousness, and seizures or convulsions.

Give GVOKE HypoPen if:

1. the patient is unconscious,
2. the patient is unable to eat sugar or a sugar-sweetened product,
3. the patient is having a seizure, or
4. you have tried to give the patient sugar or drinks that are high in sugar such as a regular soft drink (soda) or fruit juice and the patient does not get better.

Milder cases of hypoglycemia should be treated promptly by eating sugar or a sugar sweetened product. (See Information on Hypoglycemia for more information on the symptoms of low blood sugar.) GVOKE HypoPen will not work when taken by mouth (orally).

Information on Hypoglycemia

Early symptoms of hypoglycemia (low blood sugar) include:

- sweating
- drowsiness
- dizziness
- sleep disturbances
- palpitation
- anxiety
- tremor
- light-headedness
- abnormal behavior
- inability to concentrate

- blurred vision
- hunger
- slurred speech
- depressed mood
- tingling in the hands, feet, lips, or tongue
- irritability
- unsteady movement
- headache
- personality changes

If not treated, the patient may progress to severe hypoglycemia which can include:

- confusion
- seizures
- unconsciousness
- death

The occurrence of early symptoms calls for quick and, if necessary, repeated administration of some form of carbohydrate. Patients should always carry a quick source of sugar, such as candy mints or glucose tablets. The prompt treatment of mild hypoglycemic symptoms can prevent severe hypoglycemic reactions. If the patient does not improve or if administration of carbohydrate is impossible, GVOKE HypoPen® should be given or the patient should be treated with intravenous glucose by a medical professional.

Possible Problems with GVOKE HypoPen Treatment

Common side effects in adults and pediatric patients are nausea and vomiting. The product may cause serious side effects including serious allergic reactions, fast heart beat and high blood pressure.

People may be allergic to glucagon or to one of the inactive ingredients in GVOKE HypoPen or may experience fast heart-beat for a short while.

If you experience any other reactions that may have been caused by GVOKE HypoPen, please contact your healthcare provider.

Important:

- Act quickly. Prolonged unconsciousness may be harmful.
- After the injection is complete, turn the unconscious patient on his or her side to prevent them from choking in case they throw up (vomit).
- Carefully read and follow these instructions. Have a healthcare provider show you the right way to use GVOKE HypoPen.

Important Warnings

- Do not open pouch until time of use.
- Do not use after the expiration date has passed.
- Do not use if the red needle cap has been removed or is damaged.
- Do not remove the red cap until you are ready to inject.
- Do not put or press thumb, fingers, or hand over the yellow needle guard.
- Call a healthcare provider as soon as glucagon has been injected.
- If the patient does not wake up within 15 minutes, give another dose of GVOKE HypoPen® and call for emergency medical help right away.
- Feed the patient as soon as he or she wakes up and is able to swallow.

Read and become familiar with the following instructions before an emergency happens. If you have questions about using GVOKE HypoPen, talk with your healthcare provider or pharmacist.

3. PREPARING TO INJECT GVOKE HYPOPEN

Step 1. Remove GVOKE HypoPen from Foil Pouch

- Tear open pouch at the dotted line and carefully remove GVOKE HypoPen (see Figure 1).

Figure 1

Step 2. Check the Expiration Date

- Check the expiration date printed on the label of GVOKE HypoPen (see Figure 2).
- Important: Do not use GVOKE HypoPen if the expiration date has passed. If GVOKE HypoPen is expired, throw it away in an FDA cleared sharps container and use a new GVOKE HypoPen.

Figure 2

Step 3. Inspect the Solution

- Look at the liquid medicine through the viewing window. It must be clear and colorless, or a pale yellow (see Figure 3).
- Important: Do not use GVOKE HypoPen ® or inject if the liquid contains lumps, flakes, or particles. Do not inject if solution is not visible in the viewing window.
- If you do not have another GVOKE HypoPen to use, call for emergency help right away.

Figure 3

4. INJECTING GVOKE HYPOPEN

Step 4. Pull Off Red Cap

- Pull the red needle cap straight off the device (see Figure 4).
- Important: Do not put your thumb, fingers, or hand on or near the needle guard or needle opening to help prevent accidental needle sticks.

Figure 4

Step 5. Choose Injection Site and Expose Bare Skin

- Choose the lower abdomen, outer thigh, or outer upper arm for your injection site (see Figure 5).
- Remove any clothing covering the injection site (see Figure 6). The injection must be performed straight into the skin.
- Important: Do not inject through clothing.

Figure 5

Figure 6

Step 6. Push and Hold to Start Injection

- Push and hold GVOKE HypoPen® straight down against the injection site. Listen for a “Click”.
- Continue to hold the device down and count slowly to 5 (see Figure 7).
- When the injection is complete, the viewing window will be red (see Figure 8).
- Important: Do not lift up GVOKE HypoPen until the injection is complete.

Figure 7

Figure 8

Step 7. Lift Away from Skin

Lift the device straight up from the injection site (see Figure 9).

- The yellow needle guard will lock over the needle.

Figure 9

Step 8. Turn Patient onto Side

- When an unconscious person wakes up, he or she may throw up (vomit).
- Turn the unconscious patient on their side to prevent choking (see Figure 10).

Figure 10

Step 9. Make Sure Patient Receives Immediate Medical Attention After Use

- Call for emergency medical help right after GVOKE HypoPen® has been injected.
- Even if GVOKE HypoPen helps the patient to wake up, you should still call for emergency medical help right away.
- The patient’s healthcare provider should also be notified whenever a severe drop in blood sugar (hypoglycemic reactions) happens. Hypoglycemia may happen again after receiving an injection from GVOKE HypoPen. The patient’s diabetes medicine may need to be changed.
- Feed the patient as soon as he or she wakes up and is able to swallow. Give the patient a fast-acting source of sugar (such as a regular soft drink or fruit juice) and a longacting source of sugar (such as crackers and cheese or a meat sandwich). If the patient does not wake up within 15 minutes, give another dose of glucagon if a second GVOKE HypoPen is available and notify emergency medical services right away.

5. STORING GVOKE HYPOPEN

Storage Information

- Store in sealed original foil pouch until time of use.
- Store at room temperature, 68° to 77°F (20° to 25°C).
- Do not refrigerate or freeze.

6. DISPOSING OF GVOKE HYPOPEN®

Re-cap and Dispose of GVOKE HypoPen in an FDA Cleared Sharps Disposal Container

If a puncture-resistant sharps container is not available, carefully re-cap and store GVOKE HypoPen in a safe place until it can be disposed of into a FDA cleared sharps container (see Figure 11).

- Do not throw away (dispose of) loose needles and syringes in your household trash. If you do not have a FDA cleared sharps disposal container, you may use a household container that is:
- made of a heavy-duty plastic
- can be closed with a tight-fitting puncture-resistant lid, without sharps being able to come out
- upright and stable during use
- leak-resistant
- properly labeled to warn of hazardous waste inside the container.

When your sharps disposal container is almost full, you will need to follow your community guidelines for the right way to dispose of your sharps disposal container. There may be state or local laws about how you should throw away used needles and syringes. For more information about safe sharps disposal, and for specific information about sharps disposal in the state that you live in, go to the FDA’s website at: http://www.fda.gov/safesharpsdisposal.

Do not dispose of your used sharps disposal container in your household trash unless your community guidelines permit this. Always keep the sharps container out of the reach of children. If needed, make sure to get a refill of GVOKE HypoPen.

Figure 11

7. ADDITIONAL INFORMATION

This Instructions for Use has been approved by the U.S. Food and Drug Administration.

Distributed by:
Xeris Pharmaceuticals, Inc.
Chicago, IL 60607

Revised 04/2023

©2023 by Xeris Pharmaceuticals, Inc.

INSTRUCTIONS FOR USE

GVOKE® PFS
[GEE-voke P-F-S ]
(glucagon injection)
pre-filled syringe
for subcutaneous use

This “Instructions for Use” contains information on how to inject GVOKE® PFS

Section headings and other template-related items found in this IFU are for organization of the document only and are not intended for use in corresponding artwork/patient-facing IFU files. Figure numbers in this content document may not correspond to figure numbers in corresponding artwork/patient-facing IFU files.

Appropriate trademark symbol (™ or ®) should be used upon first use of a trademarked name on each page; usage may differ from this content file and final artwork based on page layout.

1. GVOKE® PFS VISUAL

Understanding GVOKE PFS

GVOKE PFS contains a 1 mg dose of glucagon and is in a foil pouch. Below is a picture of the pouch. See the GVOKE PFS package for a full view of the Quick-Use Guide.

GVOKE PFS (1 mg dose)

PFS Device

Note: GVOKE PFS should be used one time and then thrown away (discarded).

2. IMPORTANT INFORMATION YOU NEED TO KNOW BEFORE INJECTING GVOKE® PFS

- Become familiar with the following instructions before an emergency happens.
- Do not use this product past the expiration date printed on the device. Replace GVOKE PFS before the expiration date on the box.
- If you have questions regarding the use of this product, talk to a healthcare provider or pharmacist.

Make sure that relatives, close friends, or caregivers know that if you become unconscious, they should call for emergency medical help right away. GVOKE PFS may have been prescribed so that relatives, close friends, and caregivers can give the injection if you become hypoglycemic (severe low blood sugar) and are unable to take sugar by mouth. If you are unconscious, GVOKE PFS can be given while awaiting medical assistance.

Show your relatives, close friends, or caregivers where you store GVOKE PFS and how to use it. They need to know how to use GVOKE PFS before an emergency situation happens.

Indications for Use

GVOKE PFS is for the treatment of severe hypoglycemia in pediatric and adult patients with diabetes ages 2 years and above. Symptoms of severe hypoglycemia include unconsciousness, and seizures or convulsions.

Give GVOKE PFS if:

1. the patient is unconscious,
2. the patient is unable to eat sugar or a sugar-sweetened product,
3. the patient is having a seizure, or
4. you have tried to give the patient sugar or drinks that are high in sugar such as a regular soft drink (soda) or fruit juice and the patient does not get better.

Milder cases of hypoglycemia should be treated promptly by eating sugar or a sugar sweetened product. (See Information on Hypoglycemia for more information on the symptoms of low blood sugar.) GVOKE PFS will not work when taken by mouth (orally).

Information on Hypoglycemia

Early symptoms of hypoglycemia (low blood sugar) include:

- sweating
- drowsiness
- dizziness
- sleep disturbances
- palpitation
- anxiety
- tremor
- light-headedness
- abnormal behavior
- inability to concentrate

- blurred vision
- hunger
- slurred speech
- depressed mood
- tingling in the hands, feet, lips, or tongue
- irritability
- unsteady movement
- headache
- personality changes

If not treated, the patient may progress to severe hypoglycemia which can include:

- confusion
- seizures
- unconsciousness
- death

The occurrence of early symptoms calls for quick and, if necessary, repeated administration of some form of carbohydrate. Patients should always carry a quick source of sugar, such as candy mints or glucose tablets. The prompt treatment of mild hypoglycemic symptoms can prevent severe hypoglycemic reactions. If the patient does not improve or if administration of carbohydrate is impossible, GVOKE® PFS should be given or the patient should be treated with intravenous glucose by a medical professional.

Possible Problems with GVOKE PFS Treatment

Common side effects in adults and pediatric patients are nausea and vomiting. The product may cause serious side effects including serious allergic reactions, fast heart beat and high blood pressure.

People may be allergic to glucagon or to one of the inactive ingredients in GVOKE PFS, or may experience fast heart-beat for a short while.

If you experience any other reactions that may have been caused by GVOKE PFS, please contact your healthcare provider.

Important:

- Act quickly. Prolonged unconsciousness may be harmful.
- After the injection is complete, turn the unconscious patient on his or her side to prevent them from choking in case they throw up (vomit).
- Carefully read and follow these instructions. Have a healthcare provider show you the right way to use GVOKE PFS.

Important Warnings

- Do not open pouch until time of use.
- Do not use after the expiration date has passed.
- Do not use if the needle cap has been removed or is damaged.
- Do not remove the needle cap until you are ready to inject.
- Do not remove the finger flange from the syringe.
- Call a healthcare provider as soon as GVOKE® PFS has been injected.
- If the patient does not wake up within 15 minutes, give another dose of GVOKE PFS and call for emergency medical help right away.
- Feed the patient as soon as he or she wakes up and is able to swallow.

Read and become familiar with the following instructions before an emergency happens. If you have questions about using GVOKE PFS, talk with your healthcare provider or pharmacist.

3. PREPARING TO INJECT GVOKE® PFS

Step 1. Remove GVOKE PFS from Foil Pouch

- Tear open pouch at the dotted line and carefully remove GVOKE PFS (see Figure 1).

Figure 1

Step 2. Check the Expiration Date

- Check the expiration date printed on the label of GVOKE PFS (see Figure 2).
- Important: Do not use GVOKE PFS if the expiration date has passed. If GVOKE PFS is expired, throw it away in an FDA cleared sharps container and use a new GVOKE PFS.

Figure 2

Step 3. Inspect the Solution

- Look at the liquid medicine through the viewing window. It must be clear and colorless, or a pale yellow (see Figure 3).
- It is normal to see air bubbles in the medicine.
- Important: Do not try to remove air bubbles before injecting.
- Do not use GVOKE® PFS or inject if the liquid contains lumps, flakes, or particles.
- Do not inject if solution is not visible in the viewing window.
- If you do not have another GVOKE PFS to use, call for emergency help right away.

Figure 3

4. INJECTING GVOKE® PFS

Step 4. Choose Injection Site and Expose Bare Skin

- Choose the lower abdomen, outer thigh, or outer upper arm for your injection site (see Figure 4).
- Remove any clothing covering the injection site (see Figure 5). The injection must be performed straight into the skin.
- Important: Do not inject through clothing

Figure 4

Figure 5

Step 5. Pull off the Needle Cap

- Pull the needle cap straight off the syringe (see Figure 6).
- Important: Do not put your thumb, fingers, or hand on or near the needle to help prevent accidental needle sticks.

Figure 6

Step 6. Pinch, Insert and Push to Start Injection

- Pinch the skin directly around the chosen injection site and keep pinching for the entire injection (see Figure 7). This is recommended to make sure a subcutaneous (under the skin) injection is given and to prevent injection into the muscle.
- Without touching the plunger, insert the needle into the skin at the injection site at a 90-degree angle (see Figure 8).
- Push the plunger down as far as it will go to inject all of the liquid medicine into the skin (see Figure 9). You want to inject the medicine very fast to help decrease the pain.
- Important: Do not aspirate (pull back on plunger rod) after inserting the needle. Push the plunger down as far as it will go. Do not lift up GVOKE® PFS until the injection is complete.

Figure 7

Figure 8

Figure 9

Step 7. Lift Away from Skin

- Lift the syringe straight up from the injection site (see Figure 10).
- Important: Do not re-cap the syringe.

Figure 10

Step 8. Turn Patient onto Side

- When an unconscious person wakes up, he or she may throw up (vomit).
- Turn the unconscious patient on their side to prevent choking (see Figure 11).

Figure 11

Step 9. Make Sure Patient Receives Immediate Medical Attention After Use

- Call for emergency medical help right after GVOKE® PFS has been injected.
- Even if GVOKE PFS helps the patient to wake up, you should still call for emergency medical help right away.
- The patient’s healthcare provider should also be notified whenever a severe drop in blood sugar (hypoglycemic reactions) happens. Hypoglycemia may happen again after receiving an injection from GVOKE PFS. The patient’s diabetes medicine may need to be changed.
- Feed the patient as soon as he or she wakes up and is able to swallow. Give the patient a fast-acting source of sugar (such as a regular soft drink or fruit juice) and a long-acting source of sugar (such as crackers and cheese or a meat sandwich). If the patient does not wake up within 15 minutes, give another dose of glucagon if a second GVOKE PFS is available and notify emergency medical services right away.

5. STORING GVOKE® PFS

Storage Information

- Store in sealed original foil pouch until time of use.
- Store at room temperature, 68° to 77°F (20° to 25°C).
- Do not refrigerate or freeze.

6. DISPOSING OF GVOKE® PFS

Dispose of GVOKE PFS in an FDA Cleared Sharps Disposal Container

To prevent injury caused from contact with the used needle, put the used syringe in a safe place until it can be disposed of into a FDA cleared sharps container right away after use (see Figure 12). Do not throw away (dispose of) loose needles and syringes in your household trash.

If you do not have a FDA cleared sharps disposal container, you may use a household container that is:

- made of a heavy-duty plastic
- can be closed with a tight-fitting puncture-resistant lid, without sharps being able to come out
- upright and stable during use
- leak-resistant
- properly labeled to warn of hazardous waste inside the container.

When your sharps disposal container is almost full, you will need to follow your community guidelines for the right way to dispose of your sharps disposal container. There may be state or local laws about how you should throw away used needles and syringes. For more information about safe sharps disposal, and for specific information about sharps disposal in the state that you live in, go to the FDA’s website at: http://www.fda.gov/safesharpsdisposal.

Do not dispose of your used sharps disposal container in your household trash unless your community guidelines permit this. Always keep the sharps container out of the reach of children. If needed, make sure to get a refill of GVOKE PFS.

Figure 12

7. ADDITIONAL INFORMATION

This Instructions for Use has been approved by the U.S. Food and Drug Administration.

Distributed by:
Xeris Pharmaceuticals, Inc.
Chicago, IL 60607

Revised 04/2023

©2023 by Xeris Pharmaceuticals, Inc.

INSTRUCTIONS FOR USE

GVOKE KIT
[GEE-voke k-it]
glucagon injection
Subcutaneous Injection
This Instructions for Use contains information on how to inject GVOKE® KIT.

Section headings and other template-related items found in this IFU are for organization of the document only and are not intended for use in corresponding artwork/patient-facing IFU files. Figure numbers in this content document may not correspond to figure numbers in artwork/patient-facing IFU files.

GVOKE ® KIT VISUAL

Understanding GVOKE KIT

GVOKE KIT contains one (1) single-dose sterile syringe (29 G x ½” needle) with markings for 0.1 mL (0.5 mg pediatric dose) and 0.2 mL (1 mg adult dose), and one single-dose vial containing 0.2 mL of solution.

STORING GVOKE KIT

Storage Information

- Store vial and pouched syringe together in original carton until time of use. Do not remove syringe from pouch until time of use.
- Store at room temperature, 68°F to 77°F (20°C to 25°C).
- Do not refrigerate or freeze.
- Protect vial from light exposure.

IMPORTANT INFORMATION YOU NEED TO KNOW BEFORE INJECTING GVOKE KIT

- Become familiar with the following instructions before an emergency happens.
- Do not use this product past the expiration date printed on the vial. Replace GVOKE® KIT before the expiration date on the box.
- If you have questions regarding the use of this product, talk to a healthcare provider or pharmacist.

Make sure that relatives, close friends, or caregivers know that if you become unconscious, they should call for emergency medical help right away. GVOKE KIT may have been prescribed so that relatives, close friends, and caregivers can give the injection if you become hypoglycemic (severe low blood sugar) and are unable to take sugar by mouth. If you are unconscious, GVOKE KIT can be given while awaiting medical assistance.

Show your relatives, close friends, or caregivers where you store GVOKE KIT and how to use it. They need to know how to use GVOKE KIT before an emergency happens.

Indications for Use

GVOKE KIT is for the treatment of severe hypoglycemia in pediatric and adult patients with diabetes ages 2 years and above. Symptoms of severe hypoglycemia include unconsciousness and seizures or convulsions.

Give GVOKE KIT if:

1. the patient is unconscious,
2. the patient is unable to eat sugar or a sugar-sweetened product,
3. the patient is having a seizure, or
4. you have tried to give the patient sugar or drinks that are high in sugar such as a regular soft drink (soda) or fruit juice and the patient does not get better.

Milder cases of hypoglycemia should be treated promptly by eating sugar or a sugar-sweetened product. (See Information on Hypoglycemia for more information on the symptoms of low blood sugar.) GVOKE KIT will not work when taken by mouth (orally).

Information on Hypoglycemia

Early symptoms of hypoglycemia (low blood sugar) include:

- sweating
- drowsiness
- dizziness
- sleep disturbances
- palpitations
- anxiety
- tremor
- blurred vision
- unsteady movement
- headache

- hunger
- slurred speech
- depressed mood
- tingling in the hands, feet, lips, or tongue
- irritability
- light-headedness
- abnormal behavior
- inability to concentrate
- personality changes

If not treated, the patient may progress to severe hypoglycemia which can include:

- confusion
- seizures
- unconsciousness
- death

The occurrence of early symptoms of hypoglycemia calls for quick and, if necessary, repeated administration of some form of carbohydrate. Patients should always carry a quick source of sugar, such as candy mints or glucose tablets. The prompt treatment of mild hypoglycemic symptoms can prevent severe hypoglycemic reactions. If the patient does not improve or if administration of carbohydrate is not possible, GVOKE® KIT should be used or the patient should be treated with intravenous glucose by a medical professional.

Possible Problems with GVOKE KIT Treatment

Common side effects in adults and pediatric patients are nausea and vomiting. The product may cause serious side effects including serious allergic reactions, fast heart-beat, and high blood pressure.

People may be allergic to glucagon or to one of the inactive ingredients in GVOKE KIT or may experience fast heartbeat for a short while.

If you experience any other reactions that may have been caused by GVOKE KIT, please contact your healthcare provider.

Important:

- Act quickly. Prolonged unconsciousness may be harmful.
- After the injection is complete, turn the unconscious patient on his or her side to prevent them from choking in case they throw up (vomit).
- Carefully read and follow these instructions. Have a healthcare provider show you the right way to use GVOKE KIT.

Important Warnings

- Do not remove syringe from pouch until time of use.
- Do not use after the expiration date has passed.
- Do not use if the needle cap has been removed or is damaged.
- Draw the correct dose of Gvoke: 0.1 mL for pediatric patients aged 2 to under 12 years of age weighing less than 45 kg (100 lbs) and 0.2 mL for adults and pediatric patients aged 12 years and older or pediatric patients weighing 45 kg (100 lbs) or greater.
- There will be unused medicine in the vial after use. Do not save unused medicine for later use. Throw away (discard) unused portion
- Call a healthcare provider as soon as glucagon has been injected.
- If the patient does not wake up within 15 minutes, give another dose of GVOKE® KIT and call for emergency medical help right away.
- Feed the patient as soon as he or she wakes up and is able to swallow.

Read and become familiar with the following instructions before an emergency happens. If you have questions about using GVOKE KIT, talk with your healthcare provider or pharmacist.

PREPARING TO INJECT GVOKE KIT

Step 1. Remove GVOKE Vial and Syringe from Carton

- Open carton and carefully remove GVOKE vial and syringe (see Figure A).

Figure A

Step 2. Check the Expiration Date on GVOKE Vial

- Check the expiration date printed on the label of the GVOKE vial (see Figure B).
- Important: Do not use the GVOKE vial if the expiration date has passed. If the GVOKE vial is expired, discard and use a new GVOKE KIT. If you do not have another GVOKE KIT to use call for emergency medical help right away.

Figure B

Step 3. Inspect the Solution in GVOKE® Vial

- Look at the liquid medicine in the vial. It must be clear and colorless, or a pale yellow (see Figure C).
- Important: Do not use GVOKE or inject if the liquid contains lumps, flakes, or particles.

Figure C

Step 4. Prepare

- Remove the blue cap from the vial to expose the rubber stopper (see Figure D).

Figure D

- Tear Open Pouch at Dotted Line (see Figure E). Remove syringe.

Figure E

- Pull the needle cap straight off the syringe (see Figure F).
- Important: Do not put your thumb, fingers, or hand on or near the needle to help prevent accidental needle sticks.

Figure F

- Push the needle fully into the center of the rubber stopper (see Figure G). It is important to make sure the needle punctures within the raised circle of the stopper.

Figure G

- Flip vial and syringe so vial is on top (see Figure H).

Figure H

- Hold the vial upside down and pull the plunger out until the mark for 0.1 mL (0.5 mg pediatric dose) or 0.2 mL (1 mg adult dose) is lined up with the plunger and remove the syringe from the vial stopper (Figure I).

Figure I

- GVOKE should be administered immediately.
- Important: Avoid drawing air into the syringe. If large air bubbles are drawn into the syringe, gently press the plunger to push air bubbles back into the vial and redraw the dose.
- There will be unused medicine in the vial after use. Do not save unused medicine for later use. Throw away (discard) unused portion.

INJECTING GVOKE® KIT

Step 5. Choose Injection Site and Expose Bare Skin

- Choose the lower abdomen, outer thigh, or outer upper arm for your injection site (see Figure J).

Figure J

- Remove any clothing covering the injection site (see Figure K). The injection must be performed straight into the skin.
- Important: Do not inject through clothing.

Figure K

Step 6. Pinch, Insert, and Push to Start Injection

- Pinch the skin directly around the chosen injection site and keep pinching for the entire injection (see Figure L). This is recommended to make sure a subcutaneous (under the skin) injection is given and to prevent injection into the muscle.

Figure L

- Without touching the plunger, insert the needle into the skin at the injection site at a 90 degree angle (see Figure M).

Figure M

- Push the plunger down as far as it will go to inject all of the liquid medicine into the skin (see Figure N). You want to inject the medicine very fast to help decrease the pain.

Important: Do not aspirate (pull back on plunger rod) after inserting the needle. Do not lift up the syringe until the injection is complete.

Figure N

Step 7. Lift Away from Skin

- Lift the syringe straight up from the injection site (Figure O).
- Important: Do not re-cap the syringe.

Figure O

Step 8. Turn Patient onto Side

- When an unconscious person wakes up, he or she may throw up (vomit).
- Turn the unconscious patient on their side to prevent choking (see Figure P).

Figure P

Step 9. Make Sure Patient Receives Immediate Medical Attention After Use

- Call for emergency medical help right after GVOKE has been injected.
- Even if GVOKE® KIT helps the patient to wake up, you should still call for emergency medical help right away.
- The patient’s healthcare provider should also be notified whenever a severe drop in blood sugar (hypoglycemic reactions) happens. Hypoglycemia may happen again after receiving an injection from GVOKE KIT. The patient’s diabetes medicine may need to be changed.
- Feed the patient as soon as he or she wakes up and is able to swallow. Give the patient a fast-acting source of sugar (such as a regular soft drink or fruit juice) and a long-acting source of sugar (such as crackers and cheese or a meat sandwich).
- If the patient does not wake up within 15 minutes, give another dose of glucagon if a second GVOKE KIT is available and notify emergency medical services right away.

DISPOSING OF GVOKE KIT

Disposing of GVOKE KIT

After the injection, discard vial with unused medicine and place the used syringe in a safe place until it can be disposed of in an FDA-cleared sharps container (see Figure Q). Do not throw away (dispose of) loose needles and syringes in your household trash.

If you do not have an FDA-cleared sharps disposal container, you may use a household container that is:

- made of a heavy-duty plastic
- can be closed with a tight-fitting puncture-resistant lid, without sharps being able to come out
- upright and stable during use
- leak-resistant
- properly labeled to warn of hazardous waste inside the container

When your sharps disposal container is almost full, you will need to follow your community guidelines for the right way to dispose of your sharps disposal container. There may be state or local laws about how you should throw away used needles and syringes. For more information about safe sharps disposal, and for specific information about sharps disposal in the state that you live in, go to the FDA’s website at: http://www.fda.gov/safesharpsdisposal.

Do not dispose of your used sharps disposal container in your household trash unless your community guidelines permit this. Do not recycle your used sharps disposal container.

Always keep the sharps container out of the reach of children.

If needed, make sure to get a refill of your GVOKE KIT.

Figure Q

ADDITIONAL INFORMATION

This Instructions for Use has been approved by the U.S. Food and Drug Administration.

Distributed by:
Xeris Pharmaceuticals, Inc.
Chicago, IL 60607
Original Approval 08/2021

©2023 by Xeris Pharmaceuticals, Inc.

Gvoke Patient Package Insert

PATIENT INFORMATION

GVOKE® (Gee-voke)

(glucagon)

injection, for subcutaneous use

GVOKE (Gee-voke) VialDxTM

(glucagon)

injection, for intravenous use

What is GVOKE?
GVOKE is a prescription medicine used:

- to treat very low blood sugar (severe hypoglycemia) in people with diabetes aged 2 years and older.

It is not known if GVOKE is safe and effective in children under 2 years of age.

What is GVOKE VialDx?
GVOKE VialDx is a prescription medicine used:

- to stop stomach movement (gastrointestinal motility inhibitor) in adults receiving radiology exams.

It is not known if GVOKE VialDx is safe and effective in children.

Do not use GVOKE or receive Gvoke VialDx if you:

- have a tumor in the gland on top of your kidneys (adrenal gland) called pheochromocytoma.
- have a tumor in your pancreas called insulinoma.
- have had an allergic reaction to glucagon or any of the ingredients in GVOKE, or Gvoke VialDx. See the end of this Patient Information leaflet for a complete list of ingredients in GVOKE and Gvoke VialDx.

Do not receive GVOKE VialDx if you::

- have tumors in your pancreas called Glucagonomas

Before using GVOKE or receiving Gvoke VialDx, tell your healthcare provider about all of your medical conditions, including if you:

- have adrenal gland problems.
- have a tumor in your pancreas.
- have not had food or water for a long time (prolonged fasting or starvation).
- have low blood sugar that does not go away (chronic hypoglycemia).
- have diabetes mellitus
- have heart problems
- are pregnant or plan to become pregnant. It is not known if GVOKE or GVOKE VialDx will harm your unborn baby
- are breastfeeding or plan to breastfeed. It is not known if GVOKE passes into your breast milk. You and your healthcare provider should decide if you can use GVOKE while breastfeeding.

Tell your healthcare provider about all the medicines you take, including prescription and over-the-counter medicines, vitamins, and herbal supplements. GVOKE and Gvoke VialDx may affect the way other medicines work, and other medicines may affect how GVOKE and Gvoke VialDx works. Know the medicines you take. Keep a list of them to show your healthcare provider and pharmacist when you get a new medicine.

How should I use GVOKE?

- Read the detailed Instructions for Use that comes with GVOKE.
- Use GVOKE exactly how your healthcare provider tells you to use it.
- Make sure your relatives, close friends, and caregivers know where you store GVOKE and how to use it the right way before you need their help.
- Act quickly. Having very low blood sugar for a period of time may be harmful.
- After giving GVOKE, your caregiver should call for emergency medical help right away.
- When you are able to safely swallow food or drink, your caregiver should give you a fast-acting source of sugar (such as a regular soft drink or fruit juice) and a long-acting source of sugar (such as crackers and cheese or a meat sandwich).
- If you do not respond to treatment after 15 minutes, your caregiver may give you another dose, if available.

Tell your healthcare provider each time you use GVOKE. Low blood sugar may happen again after receiving an injection of GVOKE. Your diabetes medicine may need to be changed.
How will I receive Gvoke VialDx?

- GVOKE VialDx will be given by a healthcare provider through a needle placed in your vein (IV infusion).

What are the possible side effects of GVOKE and Gvoke VialDx?

GVOKE and Gvoke VialDx may cause serious side effects, including:

- high blood pressure. GVOKE and Gvoke VialDx can cause high blood pressure in certain people with tumors in their adrenal glands.
- low blood sugar. GVOKE and Gvoke VialDx can cause low blood sugar in people with certain tumors in their pancreas called insulinomas by making too much insulin in their bodies. Signs and symptoms of low blood sugar may include:

- sweating
- drowsiness
- dizziness
- sleep disturbances
- irregular heartbeat
- anxiety
- tremor

- blurred vision
- hunger
- slurred speech
- restlessness
- depressed mood
- tingling in the hands, feet, lips, or tongue
- irritability

- abnormal behavior
- lightheadedness
- unsteady movement
- inability to concentrate
- personality changes
- headache

- serious allergic reaction. Serious allergic reactions have happened in some people using products with glucagon, the active ingredient in GVOKE and GVOKE VialDx. Stop using GVOKE and call your healthcare provider or get medical help right away if you have a serious allergic reaction. If you are receiving GVOKE VialDx for a radiology exam and have a serious allergic reaction, your healthcare provider will stop the IV infusion.
  Symptoms of a serious allergic reaction include:

- rash

- difficulty breathing

- low blood pressure

- high blood sugar with GVOKE VialDx. If you have diabetes and receive GVOKE VialDx before your radiology exam it can cause high blood sugar. Your healthcare provider will check your blood sugar levels during treatment with GVOKE VialDx.

- heart problems with GVOKE VialDx.If you have heart problems and receive GVOKE VialDx before your radiology exam, you may have an increase in your blood pressure and pulse while receiving GVOKE VialDx. This could be life threatening. Your healthcare provider will monitor your heart during treatment with GVOKE VialDx.

The most common side effects of GVOKE in adults include:

- nausea
- vomiting

- swelling at the injection site
- headache

The most common side effects of GVOKE in children include:

- nausea
- low blood sugar

- high blood sugar
- vomiting

- abdominal pain
- headache

- pain or redness at the injection site
- itching

The most common side effects of GVOKE VialDx include:

- nausea
- dizziness

- change in the way foods taste or loss of taste (dysgeusia)
- hot flush

- headache

These are not all the possible side effects of GVOKE and GVOKE VialDX. Call your doctor for medical advice about side effects. You may report side effects to FDA at 1-800-FDA-1088.

How should I store GVOKE?

- Store GVOKE in the original container until time of use.
- Store at room temperature between 68°F to 77°F (20° C to 25°C).
- Do not refrigerate or freeze.

Keep GVOKE and all medicines out of the reach of children.

General information about the safe and effective use of GVOKE.

Medicines are sometimes prescribed for purposes other than those listed in a Patient Information leaflet. Do not use GVOKE for a condition for which it was not prescribed. Do not give GVOKE to other people, even if they have the same symptoms that you have. It may harm them. You can ask your pharmacist or healthcare provider for information about GVOKE that is written for health professionals.

What are the ingredients in GVOKE and GVOKE VialDx?

Active ingredient: glucagon.

Inactive ingredients: trehalose dihydrate NF, sulfuric acid NF, mannitol USP (Gvoke Kit and Gvoke VialDx only), and dimethyl sulfoxide.

GVOKE is distributed by: Xeris Pharmaceuticals, Inc., Chicago, IL

For more information go to www.xerispharma.com or call 1-877-937-4737.

GVOKE VialDx is distributed by American Regent, Inc.

This Patient Information has been approved by the U.S. Food and Drug Administration. Issued: 05/2025